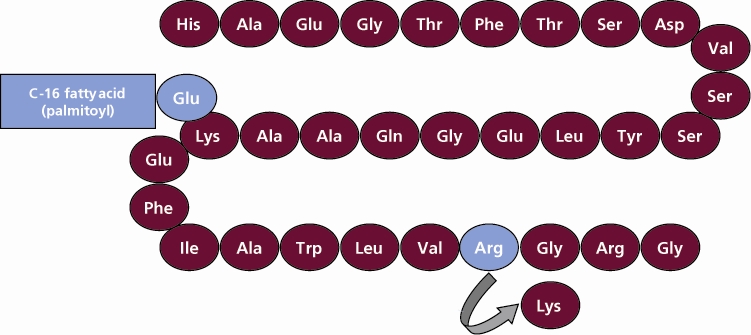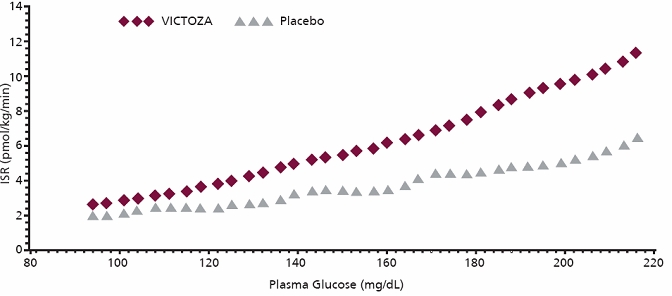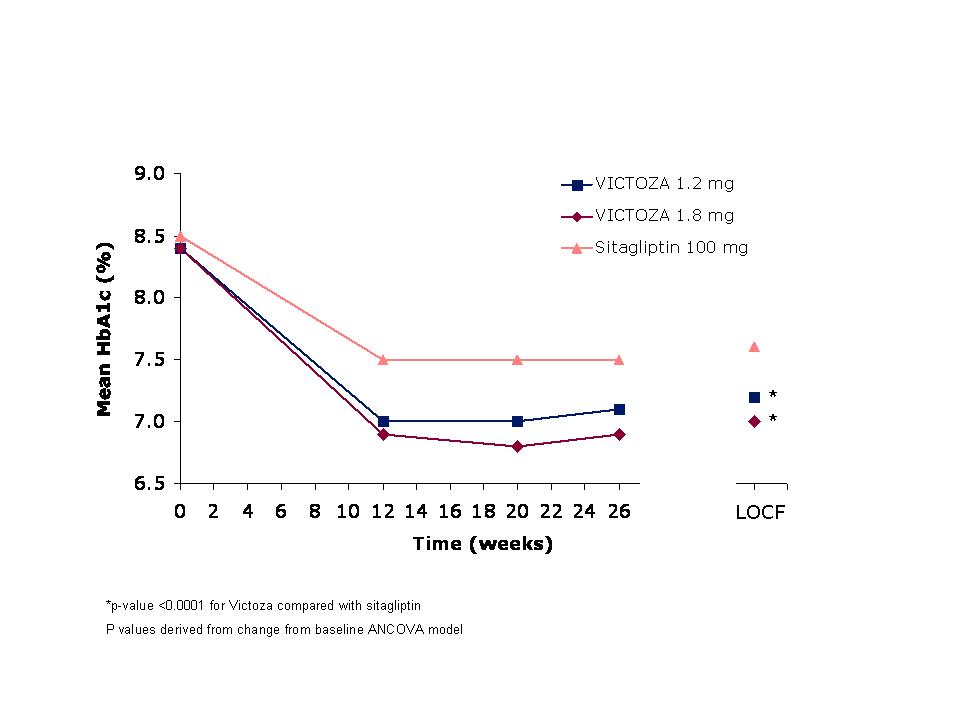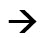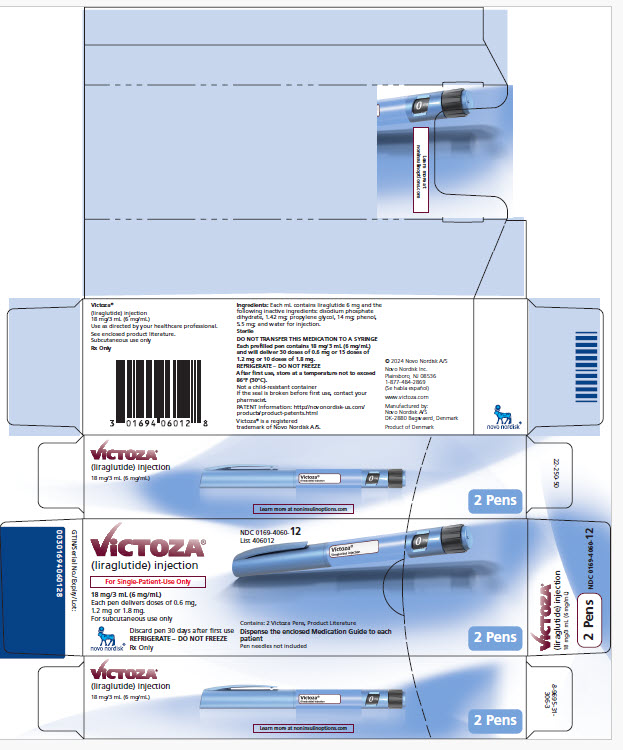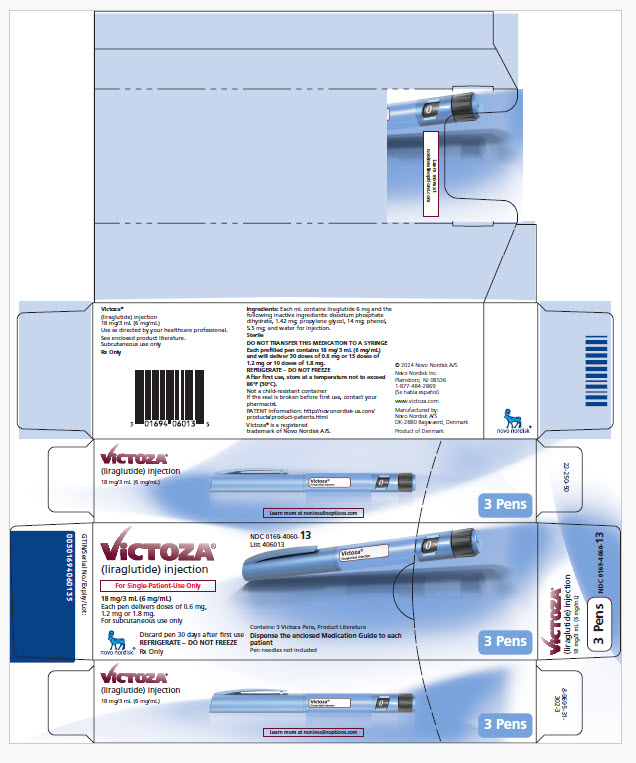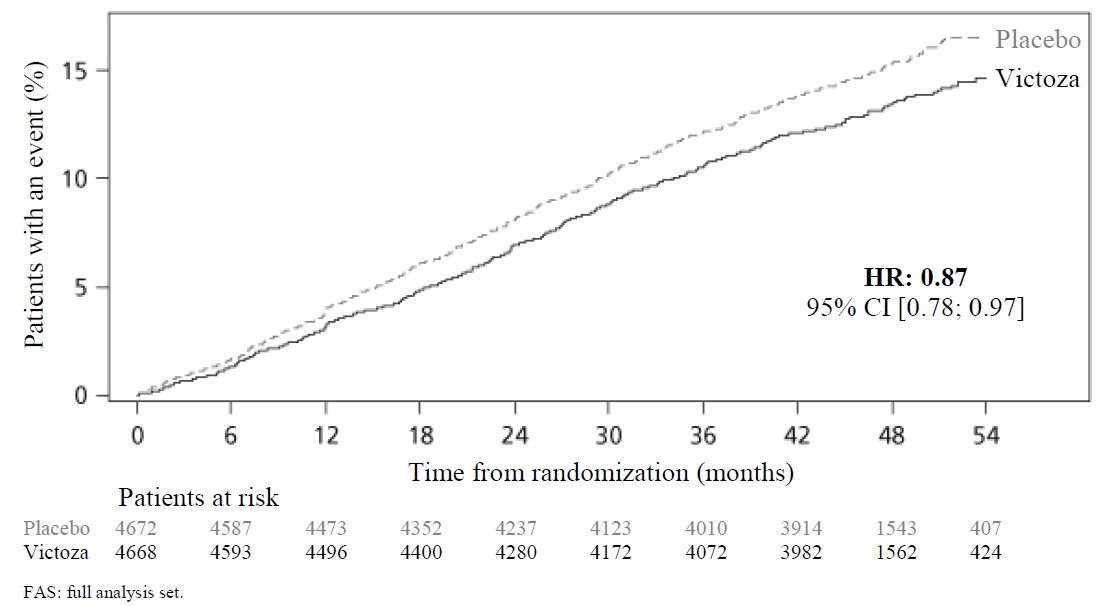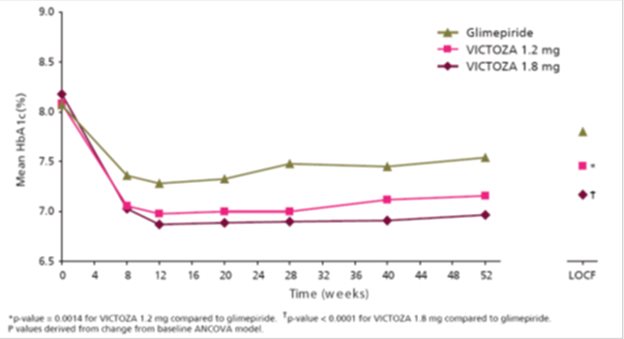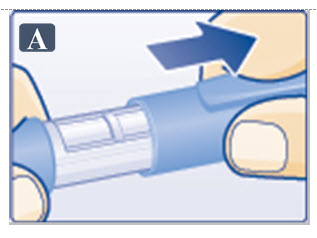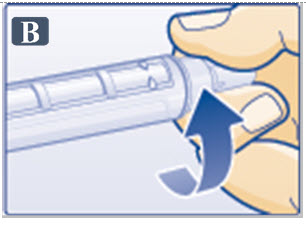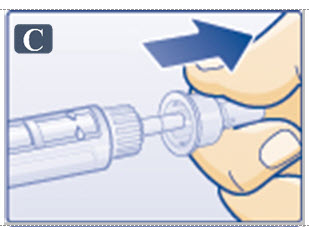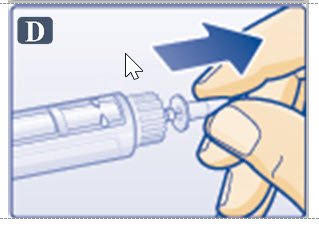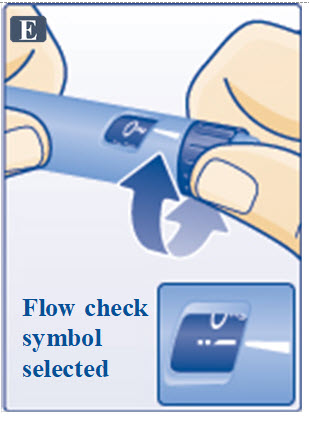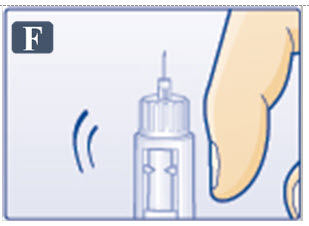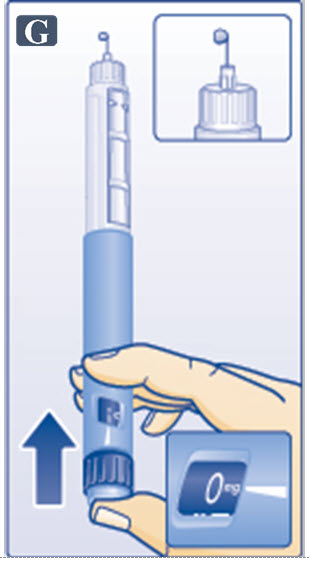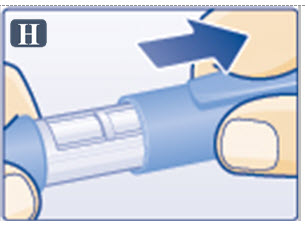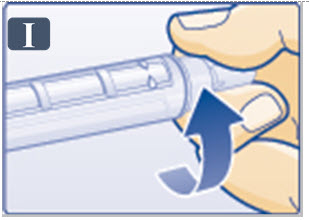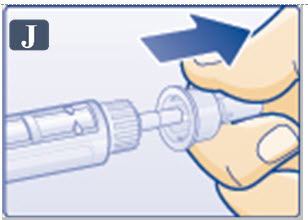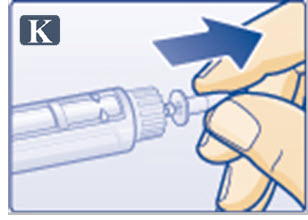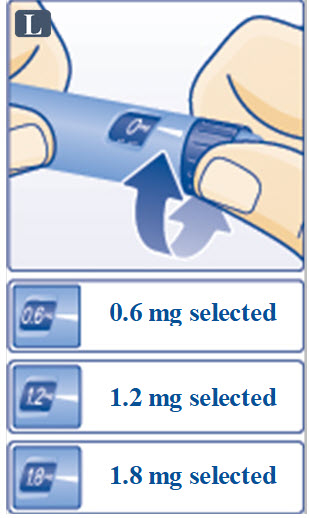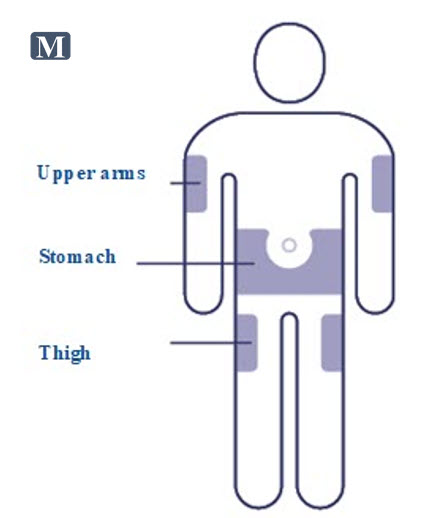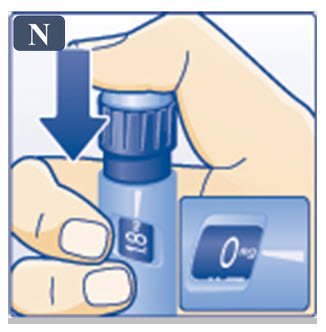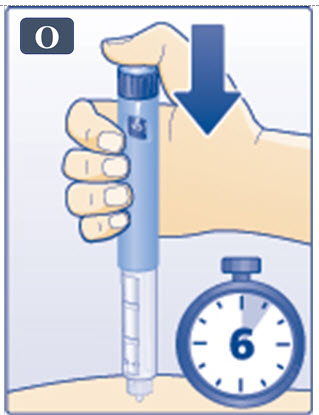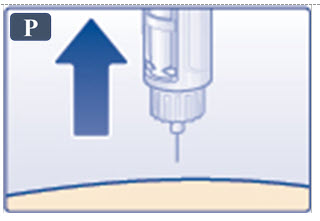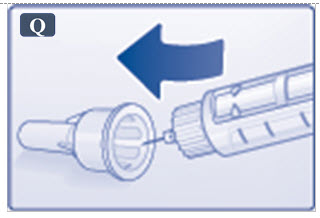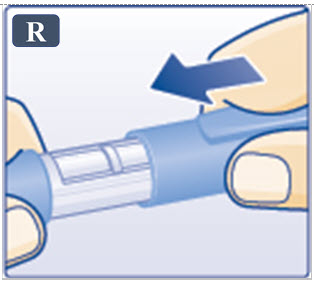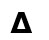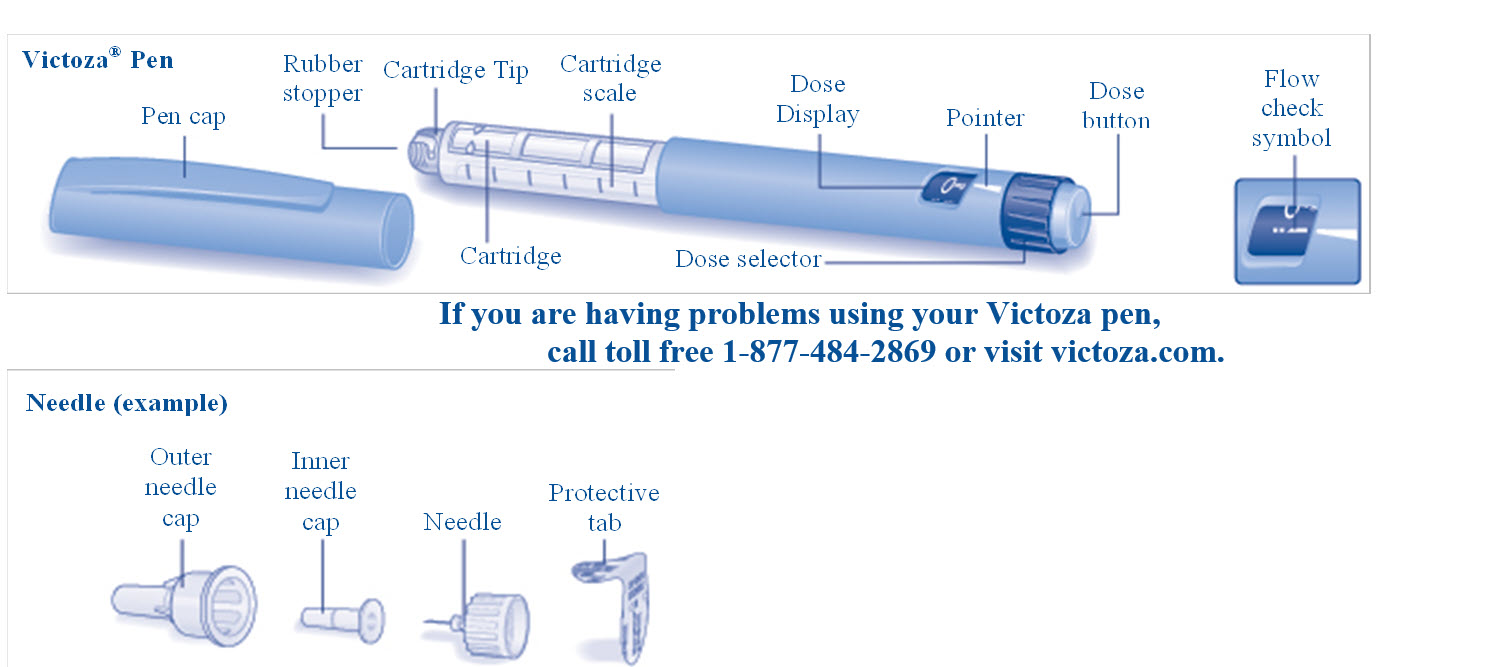 DRUG LABEL: Victoza
NDC: 0169-4060 | Form: INJECTION
Manufacturer: Novo Nordisk
Category: prescription | Type: HUMAN PRESCRIPTION DRUG LABEL
Date: 20251014

ACTIVE INGREDIENTS: LIRAGLUTIDE 6 mg/1 mL
INACTIVE INGREDIENTS: PHENOL 5.5 mg/1 mL; PROPYLENE GLYCOL 14 mg/1 mL; WATER; SODIUM PHOSPHATE, DIBASIC, DIHYDRATE 1.42 mg/1 mL

HIGHLIGHTS OF PRESCRIBING INFORMATION

These highlights do not include all the information needed to use VICTOZA® safely and effectively. See full prescribing information for VICTOZA.
VICTOZA (liraglutide) injection, for subcutaneous use
Initial U.S. Approval: 2010

RECENT MAJOR CHANGES

Indications and Usage (1)…………………………………………05/2025
Warnings and Precautions

Severe Gastrointestinal Adverse Reactions (5.6) 10/2025
  Pulmonary Aspiration During General Anesthesia
  or Deep Sedation (5.9)…………………………...……………11/2024

WARNING: RISK OF THYROID C-CELL TUMORS

See full prescribing information for complete boxed warning.

- Liraglutide causes thyroid C-cell tumors at clinically relevant exposures in both genders of rats and mice. It is unknown whether VICTOZA causes thyroid C-cell tumors, including medullary thyroid carcinoma (MTC), in humans, as the human relevance of liraglutide-induced rodent thyroid C-cell tumors has not been determined (5.1, 13.1).
- VICTOZA is contraindicated in patients with a personal or family history of MTC or in patients with Multiple Endocrine Neoplasia syndrome type 2 (MEN 2). Counsel patients regarding the potential risk of MTC and the symptoms of thyroid tumors (4, 5.1).

1 INDICATIONS AND USAGE

VICTOZA is a glucagon-like peptide-1 (GLP-1) receptor agonist indicated:

- as an adjunct to diet and exercise to improve glycemic control in adults and pediatric patients aged 10 years and older with type 2 diabetes mellitus. (1)
- to reduce the risk of major adverse cardiovascular events in adults with type 2 diabetes mellitus and established cardiovascular disease. (1)

Limitations of Use:

- Coadministration with other liraglutide-containing products is not recommended.

2 DOSAGE AND ADMINISTRATION

  - Adult Patients: Initiate at 0.6 mg injected subcutaneously once daily for one week then increase to 1.2 mg daily. If additional glycemic control is required, increase the dose to 1.8 mg daily after one week of treatment with the 1.2 mg daily dose. (2.1)
  - Pediatric Patients: Initiate at 0.6 mg injected subcutaneously once daily for at least one week. If additional glycemic control is required increase the dose to 1.2 mg daily and if additional glycemic control is still required, increase the dose to 1.8 mg daily after at least one week of treatment with the 1.2 mg daily dose. (2.1)
  - Inspect visually prior to each injection. Only use if solution is clear, colorless, and contains no particles. (2.3)
  - Inject VICTOZA subcutaneously once-daily at any time of day, independently of meals, in the abdomen, thigh or upper arm. (2.3)
  - When using VICTOZA with insulin, administer as separate injections. Never mix. (2.3)

3 DOSAGE FORMS AND STRENGTHS

Injection: 6 mg/mL solution in a prefilled, single-patient-use pen that delivers doses of 0.6 mg, 1.2 mg, or 1.8 mg. (3)

4 CONTRAINDICATIONS

- Patients with a personal or family history of medullary thyroid carcinoma or in patients with Multiple Endocrine Neoplasia syndrome type 2. (4)
- Patients with a serious hypersensitivity reaction to liraglutide or any of the excipients in VICTOZA. (4)

5 WARNINGS AND PRECAUTIONS

- Acute Pancreatitis: Has been observed in patients treated with GLP-1 receptor agonists, including VICTOZA. Discontinue if pancreatitis is suspected. (5.2)
- Never Share a VICTOZA Pen Between Patients, even if the needle is changed. (5.3)
- Hypoglycemia: Adult patients taking an insulin secretagogue or insulin may have an increased risk of hypoglycemia, including severe hypoglycemia. In pediatric patients 10 years of age and older, the risk of hypoglycemia was higher with VICTOZA regardless of insulin and/or metformin use. Reduction in the dose of insulin secretagogues or insulin may be necessary. (5.4)
- Acute Kidney Injury Due to Volume Depletion: Monitor renal function in patients reporting adverse reactions that could lead to volume depletion. (5.5)
- Severe Gastrointestinal Adverse Reactions: Use has been associated with gastrointestinal adverse reactions, sometimes severe. VICTOZA is not recommended in patients with severe gastroparesis. (5.6)
- Hypersensitivity Reactions: Postmarketing reports of serious hypersensitivity reactions (e.g., anaphylactic reactions and angioedema). Discontinue VICTOZA and promptly seek medical advice. (5.7)
- Acute Gallbladder Disease: If cholelithiasis or cholecystitis are suspected, gallbladder studies are indicated. (5.8)
- Pulmonary Aspiration During General Anesthesia or Deep Sedation: Has been reported in patients receiving GLP-1 receptor agonists undergoing elective surgeries or procedures. Instruct patients to inform healthcare providers of any planned surgeries or procedures. (5.9)

6 ADVERSE REACTIONS

- Most common adverse reactions (incidence ≥5%) in clinical trials are nausea, diarrhea, vomiting, decreased appetite, dyspepsia, constipation. (6.1)
- Immunogenicity-related events, including urticaria, were more common among VICTOZA-treated patients (0.8%) than among comparator-treated patients (0.4%) in clinical trials. (12.6)

To report SUSPECTED ADVERSE REACTIONS, contact Novo Nordisk Inc. at 1-877-484-2869 or FDA at 1-800-FDA-1088 or www.fda.gov/medwatch.

7 DRUG INTERACTIONS

Effects of delayed gastric emptying on oral medications: VICTOZA delays gastric emptying and may impact absorption of concomitantly administered oral medications. (7)

8 USE IN SPECIFIC POPULATIONS

Pregnancy: VICTOZA should be used during pregnancy only if the potential benefit justifies the potential risk to the fetus. (8.1)

FULL PRESCRIBING INFORMATION

WARNING: RISK OF THYROID C-CELL TUMORS

- Liraglutide causes dose-dependent and treatment-duration-dependent thyroid C-cell tumors at clinically relevant exposures in both genders of rats and mice. It is unknown whether VICTOZA causes thyroid C-cell tumors, including medullary thyroid carcinoma (MTC), in humans, as the human relevance of liraglutide-induced rodent thyroid C-cell tumors has not been determined [see Warnings and Precautions (5.1), Nonclinical Toxicology (13.1)].
- VICTOZA is contraindicated in patients with a personal or family history of MTC and in patients with Multiple Endocrine Neoplasia syndrome type 2 (MEN 2). Counsel patients regarding the potential risk for MTC with the use of VICTOZA and inform them of symptoms of thyroid tumors (e.g., a mass in the neck, dysphagia, dyspnea, persistent hoarseness). Routine monitoring of serum calcitonin or using thyroid ultrasound is of uncertain value for early detection of MTC in patients treated with VICTOZA [see Contraindications (4), Warnings and Precautions (5.1)].

1 INDICATIONS AND USAGE

VICTOZA is indicated:

- as an adjunct to diet and exercise to improve glycemic control in adults and pediatric patients aged 10 years and older with type 2 diabetes mellitus,
- to reduce the risk of major adverse cardiovascular events (cardiovascular death, non-fatal myocardial infarction, or non-fatal stroke) in adults with type 2 diabetes mellitus and established cardiovascular disease.

Limitations of Use:

VICTOZA contains liraglutide. Coadministration with other liraglutide-containing products is not recommended.

2 DOSAGE AND ADMINISTRATION

2.1 Recommended Dosage

Adult Patients

- The recommended starting dosage of VICTOZA is 0.6 mg injected subcutaneously once daily for one week. The 0.6 mg once daily dosage is intended to reduce the risk of gastrointestinal adverse reactions [see Warnings and Precautions (5.6), Adverse Reactions (6.1)] during initial titration and is not effective for glycemic control in adults.
- After one week at the 0.6 mg once daily dosage, increase the dosage to 1.2 mg injected subcutaneously once daily.
- If additional glycemic control is required, increase the dosage to the maximum recommended dosage of 1.8 mg injected subcutaneously once daily after at least one week of treatment with the 1.2 mg once daily dosage.

Pediatric Patients Aged 10 Years and Older

- The recommended starting dosage of VICTOZA is 0.6 mg injected subcutaneously once daily.
- If additional glycemic control is required, increase the dosage in 0.6 mg increments after at least one week on the current dosage, to reduce the risk of gastrointestinal adverse reactions [see Warnings and Precautions (5.6), Adverse Reactions (6.1)].
- The maximum recommended dosage is 1.8 mg injected subcutaneously once daily.

2.2 Recommendations Regarding Missed Dose

- Instruct patients who miss a dose of VICTOZA to resume the once daily dosage regimen as prescribed with the next scheduled dose. Do not administer an extra dose or increase the dose to make up for the missed dose.
- If more than 3 days have elapsed since the last VICTOZA dose, reinitiate VICTOZA at 0.6 mg once daily to reduce the risk of gastrointestinal adverse reactions associated with reinitiation of treatment. Upon reinitiation, VICTOZA should be titrated at the discretion of the healthcare provider.

2.3 Important Administration Instructions

- Inspect visually prior to each injection. Only use if solution is clear, colorless, and contains no particles.
- Inject VICTOZA subcutaneously once daily at any time of day, independently of meals.
- Inject VICTOZA subcutaneously in the abdomen, thigh or upper arm. No dosage adjustment is needed if changing the injection site and/or timing.
- Rotate injection sites within the same region in order to reduce the risk of cutaneous amyloidosis [see Adverse Reactions (6.2)].
- When using VICTOZA with insulin, administer as separate injections. Never mix. It is acceptable to inject VICTOZA and insulin in the same body region but the injections should not be adjacent to each other.

3 DOSAGE FORMS AND STRENGTHS

Injection: 18 mg/3 mL (6 mg/mL) clear, colorless solution in a prefilled, single-patient-use pen that delivers doses of 0.6 mg, 1.2 mg, or 1.8 mg.

4 CONTRAINDICATIONS

VICTOZA is contraindicated in patients with a:

- personal or family history of medullary thyroid carcinoma (MTC) or in patients with Multiple Endocrine Neoplasia syndrome type 2 (MEN 2) [see Warnings and Precautions (5.1)].
- serious hypersensitivity reaction to liraglutide or to any of the excipients in VICTOZA. Serious hypersensitivity reactions including anaphylactic reactions and angioedema have been reported with VICTOZA [see Warnings and Precautions (5.7)].

5 WARNINGS AND PRECAUTIONS

5.1 Risk of Thyroid C-cell Tumors

Liraglutide causes dose-dependent and treatment-duration-dependent thyroid C-cell tumors (adenomas and/or carcinomas) at clinically relevant exposures in both genders of rats and mice [see Nonclinical Toxicology (13.1)]. Malignant thyroid C-cell carcinomas were detected in rats and mice. It is unknown whether VICTOZA will cause thyroid C-cell tumors, including medullary thyroid carcinoma (MTC), in humans, as the human relevance of liraglutide-induced rodent thyroid C-cell tumors has not been determined.

Cases of MTC in patients treated with VICTOZA have been reported in the postmarketing period; the data in these reports are insufficient to establish or exclude a causal relationship between MTC and VICTOZA use in humans.

VICTOZA is contraindicated in patients with a personal or family history of MTC or in patients with MEN 2. Counsel patients regarding the potential risk for MTC with the use of VICTOZA and inform them of symptoms of thyroid tumors (e.g., a mass in the neck, dysphagia, dyspnea, persistent hoarseness).

Routine monitoring of serum calcitonin or using thyroid ultrasound is of uncertain value for early detection of MTC in patients treated with VICTOZA. Such monitoring may increase the risk of unnecessary procedures, due to low test specificity for serum calcitonin and a high background incidence of thyroid disease. Significantly elevated serum calcitonin may indicate MTC and patients with MTC usually have calcitonin values >50 ng/L. If serum calcitonin is measured and found to be elevated, the patient should be further evaluated. Patients with thyroid nodules noted on physical examination or neck imaging should also be further evaluated.

5.2 Acute Pancreatitis

Acute pancreatitis, including fatal and non-fatal hemorrhagic or necrotizing pancreatitis, has been observed in patients treated with GLP-1 receptor agonists, including liraglutide [see Adverse Reactions (6)].

After initiation of VICTOZA, observe patients carefully for signs and symptoms of acute pancreatitis which may include persistent or severe abdominal pain (sometimes radiating to the back) and which may or may not be accompanied by nausea or vomiting. If pancreatitis is suspected, discontinue VICTOZA and initiate appropriate management.

5.3 Never Share a VICTOZA Pen Between Patients

VICTOZA pens must never be shared between patients, even if the needle is changed. Pen-sharing poses a risk for transmission of blood-borne pathogens.

5.4 Hypoglycemia

Adult patients receiving VICTOZA in combination with an insulin secretagogue (e.g., sulfonylurea) or insulin may have an increased risk of hypoglycemia, including severe hypoglycemia. In pediatric patients 10 years of age and older, the risk of hypoglycemia was higher with VICTOZA regardless of insulin and/or metformin use. [see Adverse Reactions (6.1), Drug Interactions (7.2)].

The risk of hypoglycemia may be lowered by a reduction in the dose of sulfonylurea (or other concomitantly administered insulin secretagogues) or insulin. Inform patients using these concomitant medications and pediatric patients of the risk of hypoglycemia and educate them on the signs and symptoms of hypoglycemia.

5.5 Acute Kidney Injury Due to Volume Depletion

There have been postmarketing reports of acute kidney injury, in some cases requiring hemodialysis, in patients treated with VICTOZA [see Adverse Reactions (6.2)]. The majority of the reported events occurred in patients who experienced gastrointestinal reactions leading to dehydration such as nausea, vomiting, or diarrhea [see Adverse Reactions (6.1)]. Monitor renal function in patients reporting adverse reactions to VICTOZA that could lead to volume depletion, especially during dosage initiation and escalation of VICTOZA. [see Use in Specific Populations (8.6)].

5.6 Severe Gastrointestinal Adverse Reactions

Use of GLP-1 receptor agonists, including liraglutide, has been associated with gastrointestinal adverse reactions, sometimes severe [see Adverse Reactions (6)]. In VICTOZA clinical trials, severe gastrointestinal adverse reactions were reported more frequently among patients receiving VICTOZA (1.2 mg 4.4%, 1.8 mg 4.2%) than placebo (1.1%). Severe gastrointestinal adverse reactions have also been reported postmarketing with GLP-1 receptor agonists. VICTOZA is not recommended in patients with severe gastroparesis.

5.7 Hypersensitivity Reactions

There have been postmarketing reports of serious hypersensitivity reactions (e.g., anaphylactic reactions and angioedema) in patients treated with VICTOZA [see Adverse Reactions (6.2)]. If a hypersensitivity reaction occurs, discontinue VICTOZA; treat promptly per standard of care, and monitor until signs and symptoms resolve.

Anaphylaxis and angioedema have been reported with other GLP-1 receptor agonists. Use caution in a patient with a history of anaphylaxis or angioedema with another GLP-receptor agonist because it is unknown whether such patients will be predisposed to these reactions with VICTOZA. VICTOZA is contraindicated in patients who have had a serious hypersensitivity reaction to liraglutide or any of the excipients in VICTOZA [see Contraindications (4)].

5.8 Acute Gallbladder Disease

Acute events of gallbladder disease such as cholelithiasis or cholecystitis have been reported in GLP-1 receptor agonist trials and postmarketing. In the LEADER trial [see Clinical Studies (14.3)], 3.1% of VICTOZA-treated patients versus 1.9% of placebo-treated patients reported an acute event of gallbladder disease, such as cholelithiasis or cholecystitis

[see Adverse Reactions (6.1)]. If cholelithiasis is suspected, gallbladder studies and appropriate clinical follow-up are indicated.

5.9 Pulmonary Aspiration During General Anesthesia or Deep Sedation

VICTOZA delays gastric emptying [see Clinical Pharmacology (12.2)]. There have been rare postmarketing reports of pulmonary aspiration in patients receiving GLP-1 receptor agonists undergoing elective surgeries or procedures requiring general anesthesia or deep sedation who had residual gastric contents despite reported adherence to preoperative fasting recommendations.

Available data are insufficient to inform recommendations to mitigate the risk of pulmonary aspiration during general anesthesia or deep sedation in patients taking VICTOZA, including whether modifying preoperative fasting recommendations or temporarily discontinuing VICTOZA could reduce the incidence of retained gastric contents. Instruct patients to inform healthcare providers prior to any planned surgeries or procedures if they are taking VICTOZA.

6 ADVERSE REACTIONS

The following serious adverse reactions are described below or elsewhere in the prescribing information:

- Risk of Thyroid C-cell Tumors [see Warnings and Precautions (5.1)]
- Acute Pancreatitis [see Warnings and Precautions (5.2)]
- Hypoglycemia [see Warnings and Precautions (5.4)]
- Acute Kidney Injury Due to Volume Depletion [see Warnings and Precautions (5.5)]
- Severe Gastrointestinal Adverse Reactions [see Warnings and Precautions (5.6)]
- Hypersensitivity Reactions [see Warnings and Precautions (5.6)]
- Acute Gallbladder Disease [see Warnings and Precautions (5.8)]
- Pulmonary Aspiration During General Anesthesia or Deep Sedation [see Warnings and Precautions (5.9)]

6.1 Clinical Trials Experience

Because clinical trials are conducted under widely varying conditions, adverse reaction rates observed in the clinical trials of a drug cannot be directly compared to rates in the clinical trials of another drug and may not reflect the rates observed in practice.

Common Adverse Reactions

The safety of VICTOZA in patients with type 2 diabetes mellitus was evaluated in 5 glycemic control, placebo-controlled trials in adults and one trial of 52 weeks duration in pediatric patients 10 years of age and older [see Clinical Studies (14.1)]. The data in Table 1 reflect exposure of 1,673 adult patients to VICTOZA and a mean duration of exposure to VICTOZA of 37.3 weeks. The mean age of adult patients was 58 years, 4% were 75 years or older and 54% were male. The population was 79% White, 6% Black or African American, 13% Asian; 4% were of Hispanic or Latino ethnicity. At baseline the population had diabetes for an average of 9 years and a mean HbA1c of 8.4%. Baseline estimated renal function was normal or mildly impaired in 88% and moderately impaired in 12% of the pooled population.

Table 1 shows common adverse reactions in adults, excluding hypoglycemia, associated with the use of VICTOZA for the treatment of type 2 diabetes mellitus. These adverse reactions occurred more commonly on VICTOZA than on placebo and occurred in at least 5% of patients treated with VICTOZA. Overall, the type, and severity of adverse reactions in pediatric patients 10 years of age and older and above were comparable to that observed in the adult population.

Table 1. Adverse reactions reported in ≥5% of Adult Patients Treated with VICTOZA for Type 2 Diabetes Mellitus

 | Placebo; N=661 | Liraglutide 1.2 mg; N= 645 | Liraglutide 1.8 mg; N= 1024
Adverse Reaction | (%) | (%) | (%)
Nausea | 5 | 18 | 20
Diarrhea | 4 | 10 | 12
Headache | 7 | 11 | 10
Nasopharyngitis | 8 | 9 | 10
Vomiting | 2 | 6 | 9
Decreased appetite | 1 | 10 | 9
Dyspepsia | 1 | 4 | 7
Upper Respiratory Tract Infection | 6 | 7 | 6
Constipation | 1 | 5 | 5
Back Pain | 3 | 4 | 5

Cumulative proportions were calculated combining studies using Cochran-Mantel-Haenszel weights.

In an analysis of placebo- and active-controlled trials, the types and frequency of common adverse reactions, excluding hypoglycemia, were similar to those listed in Table 1.

Other Adverse Reactions

Gastrointestinal Adverse Reactions

In the pool of 5 glycemic control, placebo-controlled adult clinical trials, withdrawals due to gastrointestinal adverse reactions, occurred in 4.3% of VICTOZA-treated patients and 0.5% of placebo-treated patients. Severe gastrointestinal adverse reactions were reported more frequently among patients receiving VICTOZA (1.2 mg 4.4%, 1.8 mg 4.2%) than placebo (1.1%). Withdrawal due to gastrointestinal adverse events mainly occurred during the first 2 to 3 months of the trials.

Injection site reactions

Injection site reactions (e.g., injection site rash, erythema) were reported in approximately 2% of VICTOZA-treated adult patients in the five double-blind, glycemic control trials of at least 26 weeks duration. Less than 0.2% of VICTOZA-treated patients discontinued due to injection site reactions.

Hypoglycemia

In 5 adult glycemic control, placebo-controlled clinical trials of at least 26 weeks duration, hypoglycemia requiring the assistance of another person for treatment occurred in 8 VICTOZA-treated patients (7.5 events per 1,000 patient-years). Of these 8 VICTOZA-treated patients, 7 patients were concomitantly using a sulfonylurea.

Table 2. Adult Incidence (%) and Rate (episodes/patient year) of Hypoglycemia in 26-Week Combination Therapy Placebo-controlled Trials
 | Placebo Comparator | VICTOZA Treatment
Add-on to; Metformin | Placebo + Metformin; (N=121) | VICTOZA + Metformin; (N=724)
Patient not able to self-treat | 0 | 0.1 (0.001)
Patient able to self-treat | 2.5 (0.06) | 3.6 (0.05)
Add-on to; Glimepiride | Placebo + Glimepiride (N=114) | VICTOZA + Glimepiride (N=695)
Patient not able to self-treat | 0 | 0.1 (0.003)
Patient able to self-treat | 2.6 (0.17) | 7.5 (0.38)
Not classified | 0 | 0.9 (0.05)
Add-on to; Metformin + Rosiglitazone | Placebo + Metformin + Rosiglitazone; (N=175) | VICTOZA + Metformin +; Rosiglitazone; (N=355)
Patient not able to self-treat | 0 | 0
Patient able to self-treat | 4.6 (0.15) | 7.9 (0.49)
Not classified | 1.1 (0.03) | 0.6 (0.01)
Add-on to; Metformin + Glimepiride | Placebo + Metformin + Glimepiride; (N=114) | VICTOZA + Metformin +; Glimepiride; (N=230)
Patient not able to self-treat | 0 | 2.2 (0.06)
Patient able to self-treat | 16.7 (0.95) | 27.4 (1.16)
Not classified | 0 | 0

“Patient not able to self-treat” is defined as an event requiring the assistance of another person for treatment.

In a 26-week placebo-controlled clinical trial in pediatric patients 10 years of age and older with a 26-week open-label extension, 21.2% of VICTOZA-treated patients (mean age 14.6 years) with type 2 diabetes mellitus, had hypoglycemia with a blood glucose <54 mg/dL with or without symptoms (335 events per 1,000 patient years). No severe hypoglycemic episodes occurred in the VICTOZA treatment group (severe hypoglycemia was defined as an episode requiring assistance of another person to actively administer carbohydrate, glucagon, or other resuscitative actions).

Papillary thyroid carcinoma

In adult glycemic control trials of VICTOZA, there were 7 reported cases of papillary thyroid carcinoma in patients treated with VICTOZA and 1 case in a comparator-treated patient (1.5 vs. 0.5 cases per 1,000 patient-years). Most of these papillary thyroid carcinomas were <1 cm in greatest diameter and were diagnosed in surgical pathology specimens after thyroidectomy prompted by findings on protocol-specified screening with serum calcitonin or thyroid ultrasound.

Pancreatitis

In glycemic control trials of VICTOZA, there have been 13 cases of pancreatitis among VICTOZA-treated patients and 1 case in a comparator (glimepiride) treated patient (2.7 vs. 0.5 cases per 1,000 patient-years). Nine of the 13 cases with VICTOZA were reported as acute pancreatitis and four were reported as chronic pancreatitis. In one case in a VICTOZA-treated patient, pancreatitis, with necrosis, was observed and led to death; however clinical causality could not be established. Some patients had other risk factors for pancreatitis, such as a history of cholelithiasis or alcohol abuse.

Cholelithiasis and cholecystitis

In adult glycemic control trials of VICTOZA, the incidence of cholelithiasis was 0.3% in both VICTOZA-treated and placebo-treated patients. The incidence of cholecystitis was 0.2% in both VICTOZA-treated and placebo-treated patients.

In the LEADER trial [see Clinical Studies (14.3)], the incidence of cholelithiasis was 1.5% (3.9 cases per 1,000 patient years of observation) in adult VICTOZA-treated and 1.1% (2.8 cases per 1,000 patient years of observation) in placebo-treated patients, both on a background of standard of care. The incidence of acute cholecystitis was 1.1% (2.9 cases per 1,000 patient years of observation) in adult VICTOZA-treated and 0.7% (1.9 cases per 1,000 patient years of observation) in placebo-treated patients. The majority of events required hospitalization or cholecystectomy.

Laboratory Tests

Bilirubin

In the five adult glycemic control trials of at least 26 weeks duration, mildly elevated serum bilirubin concentrations (elevations to no more than twice the upper limit of the reference range) occurred in 4% of VICTOZA-treated patients, 2.1% of placebo-treated patients and 3.5% of active-comparator-treated patients. This finding was not accompanied by abnormalities in other liver tests. The significance of this isolated finding is unknown.

Calcitonin

Calcitonin, a biological marker of MTC, was measured throughout the clinical development program. At the end of the adult glycemic control trials, adjusted mean serum calcitonin concentrations were higher in VICTOZA-treated patients compared to placebo-treated patients but not compared to patients receiving active comparator. Between group differences in adjusted mean serum calcitonin values were approximately 0.1 ng/L or less. Among adult patients with pretreatment calcitonin <20 ng/L, calcitonin elevations to >20 ng/L occurred in 0.7% of VICTOZA-treated patients, 0.3% of placebo-treated patients, and 0.5% of active-comparator-treated patients. The clinical significance of these findings is unknown.

Lipase and Amylase

In one adult glycemic control trial in renal impairment patients, a mean increase of 33% for lipase and 15% for amylase from baseline was observed for VICTOZA-treated patients while placebo-treated patients had a mean decrease in lipase of 3% and a mean increase in amylase of 1%.

In the LEADER trial, serum lipase and amylase were routinely measured. Among adult VICTOZA-treated patients, 7.9% had a lipase value at any time during treatment of greater than or equal to 3 times the upper limit of normal compared with 4.5% of placebo-treated patients, and 1% of VICTOZA-treated patients had an amylase value at any time during treatment of greater than or equal to 3 times the upper limit of normal versus 0.7% of placebo-treated patients.

The clinical significance of elevations in lipase or amylase with VICTOZA is unknown in the absence of other signs and symptoms of pancreatitis [see Warnings and Precautions (5.2)].

Vital signs

VICTOZA did not have adverse effects on blood pressure. Mean increases from baseline in heart rate of 2 to 3 beats per minute have been observed in adult patients treated with VICTOZA compared to placebo.

6.2 Postmarketing Experience

The following additional adverse reactions have been reported during post-approval use of VICTOZA. Because these events are reported voluntarily from a population of uncertain size, it is generally not possible to reliably estimate their frequency or establish a causal relationship to drug exposure.

- Gastrointestinal: Acute pancreatitis; hemorrhagic and necrotizing pancreatitis sometimes resulting in death; ileus, intestinal obstruction, severe constipation including fecal impaction, nausea, vomiting and diarrhea leading to dehydration
- Hepatobiliary: Elevations of liver enzymes, hyperbilirubinemia, cholestasis, cholecystitis, cholelithiasis requiring cholecystectomy, hepatitis
- Hypersensitivity: Angioedema, anaphylactic reactions, pruritus
- Neoplasms: Medullary thyroid carcinoma
- Neurologic: Dysgeusia, dizziness, dysesthesia
- Pulmonary: Pulmonary aspiration has occurred in patients receiving GLP-1 receptor agonists undergoing elective surgeries or procedures requiring general anesthesia or deep sedation.
- Renal: Acute renal failure or worsening of chronic renal failure, sometimes requiring hemodialysis; and increased serum creatinine
- Skin and subcutaneous tissue: Cutaneous amyloidosis, alopecia

7 DRUG INTERACTIONS

7.1 Effects of Delayed Gastric Emptying on Oral Medications

VICTOZA causes a delay of gastric emptying, and thereby has the potential to impact the absorption of concomitantly administered oral medications. In clinical pharmacology trials, VICTOZA did not affect the absorption of the tested orally administered medications to any clinically relevant degree [see Clinical Pharmacology (12.3)]. Nonetheless, caution should be exercised when oral medications are concomitantly administered with VICTOZA.

7.2 Concomitant Use with an Insulin Secretagogue (e.g., Sulfonylurea) or with Insulin

VICTOZA stimulates insulin release in the presence of elevated blood glucose concentrations. Patients receiving VICTOZA in combination with an insulin secretagogue (e.g., sulfonylurea) or insulin may have an increased risk of hypoglycemia, including severe hypoglycemia. When initiating VICTOZA, consider reducing the dose of concomitantly administered insulin secretagogues (such as sulfonylureas) or insulin to reduce the risk of hypoglycemia [see Warnings and Precautions (5.4), Adverse Reactions (6.1)].

8 USE IN SPECIFIC POPULATIONS

8.1 Pregnancy

Risk Summary

Based on animal reproduction studies, there may be risks to the fetus from exposure to VICTOZA during pregnancy. VICTOZA should be used during pregnancy only if the potential benefit justifies the potential risk to the fetus.

Animal reproduction studies identified increased adverse developmental outcomes from exposure during pregnancy. Liraglutide exposure was associated with early embryonic deaths and an imbalance in some fetal abnormalities in pregnant rats administered liraglutide during organogenesis at doses that approximate clinical exposures at the maximum recommended human dose (MRHD) of 1.8 mg/day. In pregnant rabbits administered liraglutide during organogenesis, decreased fetal weight and an increased incidence of major fetal abnormalities were seen at exposures below the human exposures at the MRHD (see Animal Data).

The estimated background risk of major birth defects for women with uncontrolled pre-gestational diabetes (Hemoglobin A1c >7) is 6 to 10%. The major birth defect rate has been reported to be as high as 20 to 25% in women with a Hemoglobin A1c >10. In the U.S. general population, the estimated background risk of major birth defects and miscarriage in clinically recognized pregnancies is 2 to 4% and 15 to 20%, respectively.

Clinical Considerations

Disease-associated maternal and/or embryo/fetal risk

Poorly controlled diabetes in pregnancy increases the maternal risk for diabetic ketoacidosis, pre-eclampsia, spontaneous abortions, preterm delivery, and delivery complications. Poorly controlled diabetes increases the fetal risk for major birth defects, still birth, and macrosomia related morbidity.

Animal Data

Female rats given subcutaneous doses of 0.1, 0.25 and 1 mg/kg/day liraglutide beginning 2 weeks before mating through gestation day 17 had estimated systemic exposures 0.8-, 3-, and 11-times the human exposure at the MRHD based on plasma AUC comparison. The number of early embryonic deaths in the 1 mg/kg/day group increased slightly. Fetal abnormalities and variations in kidneys and blood vessels, irregular ossification of the skull, and a more complete state of ossification occurred at all doses. Mottled liver and minimally kinked ribs occurred at the highest dose. The incidence of fetal malformations in liraglutide-treated groups exceeding concurrent and historical controls were misshapen oropharynx and/or narrowed opening into larynx at 0.1 mg/kg/day and umbilical hernia at 0.1 and 0.25 mg/kg/day.

Pregnant rabbits given subcutaneous doses of 0.01, 0.025 and 0.05 mg/kg/day liraglutide from gestation day 6 through day 18 inclusive, had estimated systemic exposures less than the human exposure at the MRHD of 1.8 mg/day at all doses, based on plasma AUC. Liraglutide decreased fetal weight and dose-dependently increased the incidence of total major fetal abnormalities at all doses. The incidence of malformations exceeded concurrent and historical controls at 0.01 mg/kg/day (kidneys, scapula), ≥0.01 mg/kg/day (eyes, forelimb), 0.025 mg/kg/day (brain, tail and sacral vertebrae, major blood vessels and heart, umbilicus), ≥0.025 mg/kg/day (sternum) and at 0.05 mg/kg/day (parietal bones, major blood vessels). Irregular ossification and/or skeletal abnormalities occurred in the skull and jaw, vertebrae and ribs, sternum, pelvis, tail, and scapula; and dose-dependent minor skeletal variations were observed. Visceral abnormalities occurred in blood vessels, lung, liver, and esophagus. Bilobed or bifurcated gallbladder was seen in all treatment groups, but not in the control group.

In pregnant female rats given subcutaneous doses of 0.1, 0.25 and 1 mg/kg/day liraglutide from gestation day 6 through weaning or termination of nursing on lactation day 24, estimated systemic exposures were 0.8-, 3-, and 11-times human exposure at the MRHD of 1.8 mg/day, based on plasma AUC. A slight delay in parturition was observed in the majority of treated rats. Group mean body weight of neonatal rats from liraglutide-treated dams was lower than neonatal rats from control group dams. Bloody scabs and agitated behavior occurred in male rats descended from dams treated with 1 mg/kg/day liraglutide. Group mean body weight from birth to postpartum day 14 trended lower in F2 generation rats descended from liraglutide-treated rats compared to F2 generation rats descended from controls, but differences did not reach statistical significance for any group.

8.2 Lactation

Risk Summary

There are no data on the presence of VICTOZA in human milk, the effects on the breastfed infant, or the effects on milk production. Liraglutide was present in milk of lactating rats (see Data).

Developmental and health benefits of breastfeeding should be considered along with the mother’s clinical need for VICTOZA and any potential adverse effects on the breastfed infant from VICTOZA or from the underlying maternal condition.

Data

In lactating rats, liraglutide was present unchanged in milk at concentrations approximately 50% of maternal plasma concentrations.

8.4 Pediatric Use

The safety and effectiveness of VICTOZA as an adjunct to diet and exercise to improve glycemic control in type 2 diabetes mellitus have been established in pediatric patients 10 years of age and older. Use of VICTOZA for this indication is supported by a 26-week placebo-controlled clinical trial and a 26-week open-label extension in 134 pediatric patients 10 to 17 years of age with type 2 diabetes mellitus, a pediatric pharmacokinetic study, and studies in adults with type 2 diabetes mellitus [see Clinical Pharmacology (12.3) and Clinical Studies (14.1,14.2)]. The risk of hypoglycemia was higher with VICTOZA in pediatric patients regardless of insulin and/or metformin use [see Adverse Reactions (6.1)].

The safety and effectiveness of VICTOZA have not been established in pediatric patients less than 10 years of age.

8.5 Geriatric Use

In the VICTOZA treatment arms of the glycemic control trials, a total of 832 (19.3%) of the patients were 65 to 74 years of age and 145 (3.4%) were 75 years of age and over [see Clinical Studies (14.1)]. In the VICTOZA treatment arm of the LEADER trial [see Clinical Studies (14.3)], a total of 1738 (37.2%) patients were 65 to 74 years of age, 401 (8.6%) were 75 to 84 years of age, and 17 (0.4%) were 85 years of age or older at baseline.

No overall differences in safety or effectiveness for VICTOZA have been observed between patients 65 years of age and older and younger patients.

8.6 Renal Impairment

No dose adjustment of VICTOZA is recommended for patients with renal impairment [see Clinical Pharmacology (12.3)]. The safety and efficacy of VICTOZA was evaluated in a 26-week clinical study that included patients with moderate renal impairment (eGFR 30 to 60 mL/min/1.73 m^2) [see Clinical Studies (14.1)].

In the VICTOZA treatment arm of the LEADER trial [see Clinical Studies (14.3)], 1,932 (41.4%) patients had mild renal impairment, 999 (21.4%) patients had moderate renal impairment and 117 (2.5%) patients had severe renal impairment at baseline. No overall differences in safety or efficacy were seen in these patients compared to patients with normal renal function.

There is limited experience with VICTOZA in patients with end stage renal disease.

8.7 Hepatic Impairment

There is limited experience in patients with mild, moderate or severe hepatic impairment. Therefore, VICTOZA should be used with caution in this patient population. No dose adjustment of VICTOZA is recommended for patients with hepatic impairment [see Clinical Pharmacology (12.3)].

10 OVERDOSAGE

Overdoses have been reported in clinical trials and post-marketing use of VICTOZA. Observed effects have included severe nausea, severe vomiting, and severe hypoglycemia. In the event of overdosage, consider contacting the Poison Help line (1-800-222-1222) or a medical toxicologist for additional overdosage management recommendations. Initiate appropriate supportive treatment according to the patient’s clinical signs and symptoms.

11 DESCRIPTION

VICTOZA contains liraglutide, an analog of human GLP-1 and acts as a GLP-1 receptor agonist. The peptide precursor of liraglutide, produced by a process that includes expression of recombinant DNA in Saccharomyces cerevisiae, has been engineered to be 97% homologous to native human GLP-1 by substituting arginine for lysine at position 34. Liraglutide is made by attaching a C-16 fatty acid (palmitic acid) with a glutamic acid spacer on the remaining lysine residue at position 26 of the peptide precursor. The molecular formula of liraglutide is C172H265N43O51 and the molecular weight is 3751.2 Daltons. The structural formula (Figure 1) is:

Figure 1. Structural Formula of liraglutide

VICTOZA injection is a sterile, aqueous, clear, colorless or almost colorless solution for subcutaneous use. Each 1 mL of VICTOZA solution contains 6 mg of liraglutide and the following inactive ingredients: disodium phosphate dihydrate, 1.42 mg; propylene glycol, 14 mg; phenol, 5.5 mg; and water for injection. VICTOZA has a pH of approximately 8.15, hydrochloric acid or sodium hydroxide may be added to adjust pH. Each prefilled pen contains a 3 mL solution of VICTOZA equivalent to 18 mg liraglutide (free-base, anhydrous).

12 CLINICAL PHARMACOLOGY

12.1 Mechanism of Action

Liraglutide is an acylated human GLP-1 receptor agonist with 97% amino acid sequence homology to endogenous human GLP-1(7-37). GLP-1(7-37) represents <20% of total circulating endogenous GLP-1. Like GLP-1(7-37), liraglutide activates the GLP-1 receptor, a membrane-bound cell-surface receptor coupled to adenylyl cyclase by the stimulatory G-protein, Gs, in pancreatic beta cells. Liraglutide increases intracellular cyclic AMP (cAMP) leading to insulin release in the presence of elevated glucose concentrations. This insulin secretion subsides as blood glucose concentrations decrease and approach euglycemia. Liraglutide also decreases glucagon secretion in a glucose-dependent manner. The mechanism of blood glucose lowering also involves a delay in gastric emptying.

GLP-1(7-37) has a half-life of 1.5 to 2 minutes due to degradation by the ubiquitous endogenous enzymes, dipeptidyl peptidase 4 (DPP-4) and neutral endopeptidases (NEP). Unlike native GLP-1, liraglutide is stable against metabolic degradation by both peptidases and has a plasma half-life of 13 hours after subcutaneous administration. The pharmacokinetic profile of liraglutide, which makes it suitable for once daily administration, is a result of self-association that delays absorption, plasma protein binding and stability against metabolic degradation by DPP-4 and NEP.

12.2 Pharmacodynamics

VICTOZA’s pharmacodynamic profile is consistent with its pharmacokinetic profile observed after single subcutaneous administration as VICTOZA lowered fasting, premeal and postprandial glucose throughout the day [see Clinical Pharmacology (12.3)].

Fasting and postprandial glucose was measured before and up to 5 hours after a standardized meal after treatment to steady state with 0.6, 1.2 and 1.8 mg VICTOZA or placebo. Compared to placebo, the postprandial plasma glucose AUC0-300min was 35% lower after VICTOZA 1.2 mg and 38% lower after VICTOZA 1.8 mg.

Glucose-dependent insulin secretion

The effect of a single dose of 7.5 mcg/kg (~0.7 mg) VICTOZA on insulin secretion rates (ISR) was investigated in 10 patients with type 2 diabetes mellitus during graded glucose infusion. In these patients, on average, the ISR response was increased in a glucose-dependent manner (Figure 2).

Figure 2. Mean Insulin Secretion Rate (ISR) versus Glucose Concentration Following Single-Dose VICTOZA 7.5 mcg/kg (~ 0.7 mg) or Placebo in Patients with Type 2 Diabetes Mellitus (N=10) During Graded Glucose Infusion

Glucagon secretion

VICTOZA lowered blood glucose by stimulating insulin secretion and lowering glucagon secretion. A single dose of VICTOZA 7.5 mcg/kg (~0.7 mg) did not impair glucagon response to low glucose concentrations.

Gastric emptying

VICTOZA causes a delay of gastric emptying, thereby reducing the rate at which postprandial glucose appears in the circulation.

Cardiac Electrophysiology (QTc)

The effect of VICTOZA on cardiac repolarization was tested in a QTc study. VICTOZA at steady state concentrations with daily doses up to 1.8 mg did not produce QTc prolongation.

12.3 Pharmacokinetics

Absorption

Following subcutaneous administration, maximum concentrations of liraglutide are achieved at 8 to 12 hours post dosing. The mean peak (Cmax) and total (AUC) exposures of liraglutide were 35 ng/mL and 960 ng·h/mL, respectively, for a subcutaneous single dose of 0.6 mg. After subcutaneous single dose administrations, Cmax and AUC of liraglutide increased proportionally over the therapeutic dose range of 0.6 mg to 1.8 mg. At 1.8 mg VICTOZA, the average steady state concentration of liraglutide over 24 hours was approximately 128 ng/mL. AUC0-∞ was equivalent between upper arm and abdomen, and between upper arm and thigh. AUC0-∞ from thigh was 22% lower than that from abdomen. However, liraglutide exposures were considered comparable among these three subcutaneous injection sites. Absolute bioavailability of liraglutide following subcutaneous administration is approximately 55%.

Distribution

The mean apparent volume of distribution after subcutaneous administration of VICTOZA 0.6 mg is approximately 13 L. The mean volume of distribution after intravenous administration of VICTOZA is 0.07 L/kg. Liraglutide is extensively bound to plasma protein (>98%).

Elimination

The mean apparent clearance following subcutaneous administration of a single dose of liraglutide is approximately 1.2 L/h with an elimination half-life of approximately 13 hours.

Metabolism

During the initial 24 hours following administration of a single [^3H]-liraglutide dose to healthy subjects, the major component in plasma was intact liraglutide. Liraglutide is endogenously metabolized in a similar manner to large proteins without a specific organ as a major route of elimination.

Excretion

Following a [^3H]-liraglutide dose, intact liraglutide was not detected in urine or feces. Only a minor part of the administered radioactivity was excreted as liraglutide-related metabolites in urine or feces (6% and 5%, respectively). The majority of urine and feces radioactivity was excreted during the first 6 to 8 days.

Specific Populations

Geriatric Patients

Age had no effect on the pharmacokinetics of VICTOZA based on a pharmacokinetic study in healthy elderly subjects (65 to 83 years) and population pharmacokinetic analyses of patients 18 to 80 years of age [see Use in Specific Populations (8.5)].

Pediatric Patients

A population pharmacokinetic analysis was conducted for VICTOZA using data from 72 pediatric patients (10 to 17 years of age) with type 2 diabetes mellitus. The pharmacokinetic profile of VICTOZA in pediatric patients was consistent with that in adults.

Male and Female Patients

Based on the results of population pharmacokinetic analyses, females have 25% lower weight-adjusted clearance of VICTOZA compared to males.

Race or Ethnic Groups

Race and ethnicity had no effect on the pharmacokinetics of VICTOZA based on the results of population pharmacokinetic analyses that included White, Black or African American, Asian and Hispanic or Latino/Non-Hispanic or Latino subjects.

Body Weight

Body weight significantly affects the pharmacokinetics of VICTOZA based on results of population pharmacokinetic analyses. The exposure of liraglutide decreases with an increase in baseline body weight. However, the 1.2 mg and 1.8 mg daily doses of VICTOZA provided adequate systemic exposures over the body weight range of 40 kg to 160 kg evaluated in the clinical trials. Liraglutide was not studied in patients with body weight >160 kg.

Patients with Renal Impairment

The single-dose pharmacokinetics of VICTOZA were evaluated in patients with varying degrees of renal impairment. Patients with mild (estimated creatinine clearance 50-80 mL/min) to severe (estimated creatinine clearance <30 mL/min) renal impairment and subjects with end-stage renal disease requiring dialysis were included in the trial. Compared to healthy subjects, liraglutide AUC in mild, moderate, and severe renal impairment and in end-stage renal disease was on average 35%, 19%, 29% and 30% lower, respectively [see Use in Specific Populations (8.6)].

Patients with Hepatic Impairment

The single-dose pharmacokinetics of VICTOZA were evaluated in patients with varying degrees of hepatic impairment. Patients with mild (Child Pugh score 5-6) to severe (Child Pugh score >9) hepatic impairment were included in the trial. Compared to healthy subjects, liraglutide AUC in patients with mild, moderate and severe hepatic impairment was on average 11%, 14% and 42% lower, respectively [see Use in Specific Populations (8.7)].

Drug Interaction Studies

In vitro assessment of drug-drug interactions

VICTOZA has low potential for pharmacokinetic drug-drug interactions related to cytochrome P450 (CYP450) and plasma protein binding.

In vivo assessment of drug-drug interactions

The drug-drug interaction studies were performed at steady state with VICTOZA 1.8 mg/day. Before administration of concomitant treatment, subjects underwent a 0.6 mg weekly dose increase to reach the maximum dose of 1.8 mg/day. Administration of the interacting drugs was timed so that Cmax of VICTOZA (8 h to 12 h) would coincide with the absorption peak of the co-administered drugs.

Digoxin

A single dose of digoxin 1 mg was administered 7 hours after the dose of VICTOZA at steady state. The concomitant administration with VICTOZA resulted in a reduction of digoxin AUC by 16%; Cmax decreased by 31%. Digoxin median time to maximal concentration (Tmax) was delayed from 1 h to 1.5 h.

Lisinopril

A single dose of lisinopril 20 mg was administered 5 minutes after the dose of VICTOZA at steady state.
The coadministration with VICTOZA resulted in a reduction of lisinopril AUC by 15%; Cmax decreased by 27%. Lisinopril median Tmax was delayed from 6 h to 8 h with VICTOZA.

Atorvastatin

VICTOZA did not change the overall exposure (AUC) of atorvastatin following a single dose of atorvastatin 40 mg, administered 5 hours after the dose of VICTOZA at steady state. Atorvastatin Cmax was decreased by 38% and median Tmax was delayed from 1 h to 3 h with VICTOZA.

Acetaminophen

VICTOZA did not change the overall exposure (AUC) of acetaminophen following a single dose of acetaminophen 1000 mg, administered 8 hours after the dose of VICTOZA at steady state. Acetaminophen Cmax was decreased by 31% and median Tmax was delayed up to 15 minutes.

Griseofulvin

VICTOZA did not change the overall exposure (AUC) of griseofulvin following coadministration of a single dose of griseofulvin 500 mg with VICTOZA at steady state. Griseofulvin Cmax increased by 37% while median Tmax did not change.

Oral Contraceptives

A single dose of an oral contraceptive combination product containing 0.03 mg ethinylestradiol and 0.15 mg levonorgestrel was administered under fed conditions and 7 hours after the dose of VICTOZA at steady state. VICTOZA lowered ethinylestradiol and levonorgestrel Cmax by 12% and 13%, respectively. There was no effect of VICTOZA on the overall exposure (AUC) of ethinylestradiol. VICTOZA increased the levonorgestrel AUC0-∞ by 18%. VICTOZA delayed Tmax for both ethinylestradiol and levonorgestrel by 1.5 h.

Insulin Detemir

No pharmacokinetic interaction was observed between VICTOZA and insulin detemir when separate subcutaneous injections of insulin detemir 0.5 Unit/kg (single-dose) and VICTOZA 1.8 mg (steady state) were administered in patients with type 2 diabetes mellitus.

12.6 Immunogenicity

The observed incidence of anti-drug antibodies is highly dependent on the sensitivity and specificity of the assay. Differences in assay methods preclude meaningful comparisons of the incidence of anti-drug antibodies in the studies described below with the incidence of anti-drug antibodies in other studies, including those with VICTOZA or other liraglutide products.

A subset of VICTOZA-treated patients (1,104 of 2,501, 44%) in five adult double-blind clinical trials of 26 weeks duration or longer were tested for the presence of anti-liraglutide antibodies at the end of treatment [see Clinical Studies (14.1)] and 102/1,104 (9%) of VICTOZA-treated patients developed anti-liraglutide antibodies. Of these 102 VICTOZA-treated patients, 56 (5%) patients developed antibodies that cross-reacted with native GLP-1. These cross-reacting antibodies were not tested for neutralizing effect against native GLP-1, and thus the potential for clinically significant neutralization of native GLP-1 was not assessed. Antibodies that had a neutralizing effect on liraglutide in an in vitro assay occurred in 12 (1%) of the VICTOZA-treated patients. There was no identified clinically significant effect of anti-liraglutide antibodies on effectiveness of VICTOZA.

In five double-blind adult glycemic control trials of VICTOZA, events from a composite of adverse events potentially related to immunogenicity (e.g., urticaria, angioedema) occurred among 0.8% of VICTOZA-treated patients and among 0.4% of comparator-treated patients. Urticaria accounted for approximately one-half of the events in this composite for VICTOZA-treated patients. Patients who developed anti-liraglutide antibodies were not more likely to develop events from the immunogenicity events composite than were patients who did not develop anti-liraglutide antibodies.

In the LEADER trial [see Clinical Studies (14.3)], anti-liraglutide antibodies were detected in 11 out of the 1247 (0.9%) adult VICTOZA-treated patients with antibody measurements. Of the 11 adult VICTOZA-treated patients who developed anti-liraglutide antibodies, none were observed to develop neutralizing antibodies to liraglutide, and 5 patients (0.4%) developed cross-reacting antibodies against native GLP-1.

In a clinical trial with pediatric patients aged 10 years and older [see Clinical Studies (14.2)], anti-liraglutide antibodies were detected in 1 (2%) VICTOZA treated patient at week 26 and 5 (9%) VICTOZA treated patients at week 53. None of the 5 patients had antibodies cross reactive to native GLP-1 or had neutralizing antibodies.

13 NONCLINICAL TOXICOLOGY

13.1 Carcinogenesis, Mutagenesis, Impairment of Fertility

A 104-week carcinogenicity study was conducted in male and female CD-1 mice at doses of 0.03, 0.2, 1, and 3 mg/kg/day liraglutide administered by bolus subcutaneous injection yielding systemic exposures 0.2-, 2-, 10- and 45-times the human exposure, respectively, at the MRHD of 1.8 mg/day based on plasma AUC comparison. A dose-related increase in benign thyroid C-cell adenomas was seen in the 1 and the 3 mg/kg/day groups with incidences of 13% and 19% in males and 6% and 20% in females, respectively. C-cell adenomas did not occur in control groups or 0.03 and 0.2 mg/kg/day groups. Treatment-related malignant C-cell carcinomas occurred in 3% of females in the 3 mg/kg/day group. Thyroid C-cell tumors are rare findings during carcinogenicity testing in mice. A treatment-related increase in fibrosarcomas was seen on the dorsal skin and subcutis, the body surface used for drug injection, in males in the 3 mg/kg/day group. These fibrosarcomas were attributed to the high local concentration of drug near the injection site. The liraglutide concentration in the clinical formulation (6 mg/mL) is 10-times higher than the concentration in the formulation used to administer 3 mg/kg/day liraglutide to mice in the carcinogenicity study (0.6 mg/mL).

A 104-week carcinogenicity study was conducted in male and female Sprague Dawley rats at doses of 0.075, 0.25 and 0.75 mg/kg/day liraglutide administered by bolus subcutaneous injection with exposures 0.5-, 2- and 8-times the human exposure, respectively, resulting from the MRHD based on plasma AUC comparison. A treatment-related increase in benign thyroid C-cell adenomas was seen in males in 0.25 and 0.75 mg/kg/day liraglutide groups with incidences of 12%, 16%, 42%, and 46% and in all female liraglutide-treated groups with incidences of 10%, 27%, 33%, and 56% in 0 (control), 0.075, 0.25, and 0.75 mg/kg/day groups, respectively. A treatment-related increase in malignant thyroid C-cell carcinomas was observed in all male liraglutide-treated groups with incidences of 2%, 8%, 6%, and 14% and in females at 0.25 and 0.75 mg/kg/day with incidences of 0%, 0%, 4%, and 6% in 0 (control), 0.075, 0.25, and 0.75 mg/kg/day groups, respectively. Thyroid C-cell carcinomas are rare findings during carcinogenicity testing in rats.

Studies in mice demonstrated that liraglutide-induced C-cell proliferation was dependent on the GLP-1 receptor and that liraglutide did not cause activation of the REarranged during Transfection (RET) proto-oncogene in thyroid C-cells.

Human relevance of thyroid C-cell tumors in mice and rats is unknown and has not been determined by clinical studies or nonclinical studies [see Boxed Warning, Warnings and Precautions (5.1)].

Liraglutide was negative with and without metabolic activation in the Ames test for mutagenicity and in a human peripheral blood lymphocyte chromosome aberration test for clastogenicity. Liraglutide was negative in repeat-dose in vivo micronucleus tests in rats.

In rat fertility studies using subcutaneous doses of 0.1, 0.25 and 1 mg/kg/day liraglutide, males were treated for 4 weeks prior to and throughout mating and females were treated 2 weeks prior to and throughout mating until gestation day 17. No direct adverse effects on male fertility was observed at doses up to 1 mg/kg/day, a high dose yielding an estimated systemic exposure 11- times the human exposure at the MRHD, based on plasma AUC. In female rats, an increase in early embryonic deaths occurred at 1 mg/kg/day. Reduced body weight gain and food consumption were observed in females at the 1 mg/kg/day dose.

14 CLINICAL STUDIES

14.1 Glycemic Control Trials in Adults with Type 2 Diabetes Mellitus

In glycemic control trials in adults, VICTOZA has been studied as monotherapy and in combination with one or two oral anti-diabetic medications or basal insulin. VICTOZA was also studied in a cardiovascular outcomes trial (LEADER trial).

In each of the placebo controlled trials, treatment with VICTOZA produced clinically and statistically significant improvements in hemoglobin A1c and fasting plasma glucose (FPG) compared to placebo.

All VICTOZA-treated patients started at 0.6 mg/day. The dose was increased in weekly intervals by 0.6 mg to reach 1.2 mg or 1.8 mg for patients randomized to these higher doses. VICTOZA 0.6 mg is not effective for glycemic control and is intended only as a starting dose to reduce gastrointestinal intolerance [see Dosage and Administration (2)].

Monotherapy

In this 52-week trial, 746 adult patients with type 2 diabetes mellitus were randomized to VICTOZA 1.2 mg, VICTOZA 1.8 mg, or glimepiride 8 mg. Patients who were randomized to glimepiride were initially treated with 2 mg daily for two weeks, increasing to 4 mg daily for another two weeks, and finally increasing to 8 mg daily. Treatment with VICTOZA 1.8 mg and 1.2 mg resulted in a statistically significant reduction in HbA1c compared to glimepiride (Table 3). The percentage of patients who discontinued due to ineffective therapy was 3.6% in the VICTOZA 1.8 mg treatment group, 6% in the VICTOZA 1.2 mg treatment group, and 10.1% in the glimepiride-treatment group.

The mean age of participants was 53 years, and the mean duration of diabetes was 5 years. Participants were 49.7% male, 77.5% White, 12.6% Black or African American and 35% of Hispanic or Latino ethnicity. The mean BMI was 33.1 kg/m^2.

Table 3. Results of a 52-week Monotherapy Trial in Adults with Type 2 Diabetes Mellitusa

 | VICTOZA; 1.8 mg | VICTOZA; 1.2 mg | Glimepiride 8 mg
Intent-to-Treat Population (N) | 246 | 251 | 248
HbA1c (%) (Mean)
Baseline | 8.2 | 8.2 | 8.2
Change from baseline (adjusted mean)b | -1.1 | -0.8 | -0.5
Difference from glimepiride arm (adjusted mean)b | -0.6** | -0.3*
95% Confidence Interval | (-0.8, -0.4) | (-0.5, -0.1)
Percentage of patients achieving HbA1c <7% | 51 | 43 | 28
Fasting Plasma Glucose (mg/dL) (Mean)
Baseline | 172 | 168 | 172
Change from baseline (adjusted mean)b | -26 | -15 | -5
Difference from glimepiride arm (adjusted mean)b | -20** | -10*
95% Confidence Interval | (-29, -12) | (-19, -1)
Body Weight (kg) (Mean)
Baseline | 92.6 | 92.1 | 93.3
Change from baseline (adjusted mean)b | -2.5 | -2.1 | +1.1
Difference from glimepiride arm (adjusted mean)b | -3.6** | -3.2**
95% Confidence Interval | (-4.3, -2.9) | (-3.9, -2.5)

a Intent-to-treat population using last observation on study

b Least squares mean adjusted for baseline value

* p-value <0.05

** p-value <0.0001

Figure 3. Mean HbA1c for Adult Patients with Type 2 Diabetes Mellitus who Completed the 52-week Trial and for the Last Observation Carried Forward (LOCF, intent-to-treat) data at Week 52 (Monotherapy)

Combination Therapy

Add-on to Metformin

In this 26-week trial, 1,091 adult patients with type 2 diabetes mellitus were randomized to VICTOZA 0.6 mg, VICTOZA 1.2 mg, VICTOZA 1.8 mg, placebo, or glimepiride 4 mg (one-half of the maximal approved dose in the United States), all as add-on to metformin. Randomization occurred after a 6-week run-in period consisting of a 3-week initial forced metformin titration period followed by a maintenance period of another 3 weeks. During the titration period, doses of metformin were increased up to 2,000 mg/day. Treatment with VICTOZA 1.2 mg and 1.8 mg as add-on to metformin resulted in a significant mean HbA1c reduction relative to placebo add-on to metformin and resulted in a similar mean HbA1c reduction relative to glimepiride 4 mg add-on to metformin (Table 4). The percentage of patients who discontinued due to ineffective therapy was 5.4% in the VICTOZA 1.8 mg + metformin treatment group, 3.3% in the VICTOZA 1.2 mg + metformin treatment group, 23.8% in the placebo + metformin treatment group, and 3.7% in the glimepiride + metformin treated group.

The mean age of participants was 57 years, and the mean duration of diabetes was 7 years. Participants were 58.2% male, 87.1% White and 2.4% Black or African American. The mean BMI was 31.0 kg/m^2.

Table 4. Results of a 26-week Trial of VICTOZA as Add-on to Metformin in Adults with Type 2 Diabetes Mellitusa

 | VICTOZA; 1.8 mg +; Metformin | VICTOZA; 1.2 mg +; Metformin | Placebo + Metformin | Glimepiride 4 mg† + Metformin
Intent-to-Treat Population (N) | 242 | 240 | 121 | 242
HbA1c (%) (Mean)
Baseline | 8.4 | 8.3 | 8.4 | 8.4
Change from baseline (adjusted mean)b | -1 | -1 | +0.1 | -1
Difference from placebo + metformin arm (adjusted mean)b | -1.1** | -1.1**
95% Confidence Interval | (-1.3, -0.9) | (-1.3, -0.9)
Difference from glimepiride + metformin arm (adjusted mean)b | 0 | 0
95% Confidence Interval | (-0.2, 0.2) | (-0.2, 0.2)
Percentage of patients achieving HbA1c <7% | 42 | 35 | 11 | 36
Fasting Plasma Glucose (mg/dL) (Mean)
Baseline | 181 | 179 | 182 | 180
Change from baseline (adjusted mean)b | -30 | -30 | +7 | -24
Difference from placebo + metformin arm (adjusted mean)b | -38** | -37**
95% Confidence Interval | (-48, -27) | (-47, -26)
Difference from glimepiride + metformin arm (adjusted mean)b | -7 | -6
95% Confidence Interval | (-16, 2) | (-15, 3)
Body Weight (kg) (Mean)
Baseline | 88 | 88.5 | 91 | 89
Change from baseline (adjusted mean)b | -2.8 | -2.6 | -1.5 | +1
Difference from placebo + metformin arm (adjusted mean)b; 95% Confidence Interval | -1.3*; (-2.2, -0.4) | -1.1*; (-2, -0.2)
Difference from glimepiride + metformin arm (adjusted mean)b | -3.8** | -3.5**
95% Confidence Interval | (-4.5, -3.0) | (-4.3, -2.8)
a Intent-to-treat population using last observation on study
b Least squares mean adjusted for baseline value
† For glimepiride, one-half of the maximal approved United States dose.
* p-value <0.05
** p-value <0.0001

VICTOZA Compared to Sitagliptin, Both as Add-on to Metformin

In this 26–week, open-label trial, 665 adult patients with type 2 diabetes mellitus on a background of metformin ≥1,500 mg per day were randomized to VICTOZA 1.2 mg once daily, VICTOZA 1.8 mg once daily or sitagliptin 100 mg once daily, all dosed according to approved labeling. Patients were to continue their current treatment on metformin at a stable, pre-trial dose level and dosing frequency.

The mean age of participants was 56 years, and the mean duration of diabetes was 6 years. Participants were 52.9% male, 86.6% White, 7.2% Black or African American and 16.2% of Hispanic or Latino ethnicity. The mean BMI was 32.8 kg/m^2.

The primary endpoint was the change in HbA1c from baseline to Week 26. Treatment with VICTOZA 1.2 mg and VICTOZA 1.8 mg resulted in statistically significant reductions in HbA1c relative to sitagliptin 100 mg (Table 5). The percentage of patients who discontinued due to ineffective therapy was 3.1% in the VICTOZA 1.2 mg group, 0.5% in the VICTOZA 1.8 mg treatment group, and 4.1% in the sitagliptin 100 mg treatment group. From a mean baseline body weight of 94 kg, there was a mean reduction of 2.7 kg for VICTOZA 1.2 mg, 3.3 kg for VICTOZA 1.8 mg, and 0.8 kg for sitagliptin 100 mg.

Table 5. Results of a 26-week Open-label Trial of VICTOZA Compared to Sitagliptin (both in combination with metformin) in Adults with Type 2 Diabetes Mellitusa

 | VICTOZA; 1.8 mg +; Metformin | VICTOZA; 1.2 mg +; Metformin | Sitagliptin; 100 mg +; Metformin
Intent-to-Treat Population (N) | 218 | 221 | 219
HbA1c (%) (Mean)
Baseline | 8.4 | 8.4 | 8.5
Change from baseline (adjusted mean) | -1.5 | -1.2 | -0.9
Difference from sitagliptin arm (adjusted mean)b; 95% Confidence Interval | -0.6**; (-0.8, -0.4) | -0.3**; (-0.5, -0.2)
Percentage of patients achieving HbA1c <7% | 56 | 44 | 22
Fasting Plasma Glucose (mg/dL) (Mean)
Baseline | 179 | 182 | 180
Change from baseline (adjusted mean) | -39 | -34 | -15
Difference from sitagliptin arm (adjusted mean)b; 95% Confidence Interval | -24**; (-31, -16) | -19**; (-26, -12)

a Intent-to-treat population using last observation on study

b Least squares mean adjusted for baseline value

** p-value <0.0001

Figure 4. Mean HbA1c for Adult Patients with Type 2 Diabetes Mellitus who Completed the 26-week Trial and for the Last Observation Carried Forward (LOCF, intent-to-treat) data at Week 26

Combination Therapy with Metformin and Insulin

This 26-week open-label trial enrolled 988 adult patients with type 2 diabetes mellitus with inadequate glycemic control (HbA1c 7% to 10%) on metformin (≥1,500 mg/day) alone or inadequate glycemic control (HbA1c 7% to 8.5%) on metformin (≥1,500 mg/day) and a sulfonylurea. Patients who were on metformin and a sulfonylurea discontinued the sulfonylurea then all patients entered a 12-week run-in period during which they received add-on therapy with VICTOZA titrated to 1.8 mg once-daily. At the end of the run-in period, 498 patients (50%) achieved HbA1c <7% with VICTOZA 1.8 mg and metformin and continued treatment in a non-randomized, observational arm. Another 167 patients (17%) withdrew from the trial during the run-in period with approximately one-half of these patients doing so because of gastrointestinal adverse reactions [see Adverse Reactions (6.1)]. The remaining 323 patients with HbA1c ≥7% (33% of those who entered the run-in period) were randomized to 26 weeks of once-daily insulin detemir administered in the evening as add-on therapy (N=162) or to continued, unchanged treatment with VICTOZA 1.8 mg and metformin (N=161). The starting dose of insulin detemir was 10 units/day and the mean dose at the end of the 26-week randomized period was 39 units/day. During the 26 week randomized treatment period, the percentage of patients who discontinued due to ineffective therapy was 11.2% in the group randomized to continued treatment with VICTOZA 1.8 mg and metformin and 1.2% in the group randomized to add-on therapy with insulin detemir.

The mean age of participants was 57 years, and the mean duration of diabetes was 8 years. Participants were 55.7% male, 91.3% White, 5.6% Black or African American and 12.5% of Hispanic or Latino ethnicity. The mean BMI was 34 kg/m^2.

Treatment with insulin detemir as add-on to VICTOZA 1.8 mg + metformin resulted in statistically significant reductions in HbA1c and FPG compared to continued, unchanged treatment with VICTOZA 1.8 mg + metformin alone (Table 6). From a mean baseline body weight of 96 kg after randomization, there was a mean reduction of 0.3 kg in the patients who received insulin detemir add-on therapy compared to a mean reduction of 1.1 kg in the patients who continued on unchanged treatment with VICTOZA 1.8 mg + metformin alone.

Table 6. Results of a 26-week Open-label Trial of Insulin detemir as add on to VICTOZA + Metformin Compared to Continued Treatment with VICTOZA + Metformin alone in Adult Patients with Type 2 Diabetes Mellitus not Achieving HbA1c <7% after 12 weeks of Metformin and VICTOZAa

 | Insulin detemir + VICTOZA + Metformin | VICTOZA + Metformin
Intent-to-Treat Population (N) | 162 | 157
HbA1c (%) (Mean)
Baseline (week 0) | 7.6 | 7.6
Change from baseline (adjusted mean) | -0.5 | 0
Difference from VICTOZA + metformin arm (LS mean)b | -0.5**
95% Confidence Interval | (-0.7, -0.4)
Percentage of patients achieving HbA1c <7% | 43 | 17
Fasting Plasma Glucose (mg/dL) (Mean)
Baseline (week 0) | 166 | 159
Change from baseline (adjusted mean) | -39 | -7
Difference from VICTOZA + metformin arm (LS mean)b | -31**
95% Confidence Interval | (-39, -23)

a Intent-to-treat population using last observation on study

b Least squares mean adjusted for baseline value

** p-value <0.0001

Add-on to Sulfonylurea

In this 26-week trial, 1,041 adult patients with type 2 diabetes mellitus were randomized to VICTOZA 0.6 mg, VICTOZA 1.2 mg, VICTOZA 1.8 mg, placebo, or rosiglitazone 4 mg (one-half of the maximal approved dose in the United States), all as add-on to glimepiride. Randomization occurred after a 4-week run-in period consisting of an initial, 2-week, forced-glimepiride titration period followed by a maintenance period of another 2 weeks. During the titration period, doses of glimepiride were increased to 4 mg/day. The doses of glimepiride could be reduced (at the discretion of the investigator) from 4 mg/day to 3 mg/day or 2 mg/day (minimum) after randomization, in the event of unacceptable hypoglycemia or other adverse events.

The mean age of participants was 56 years, and the mean duration of diabetes was 8 years. Participants were 49.4% male, 64.4% White and 2.8% Black or African American. The mean BMI was 29.9 kg/m^2.

Treatment with VICTOZA 1.2 mg and 1.8 mg as add-on to glimepiride resulted in a statistically significant reduction in mean HbA1c compared to placebo add-on to glimepiride (Table 7). The percentage of patients who discontinued due to ineffective therapy was 3% in the VICTOZA 1.8 mg + glimepiride treatment group, 3.5% in the VICTOZA 1.2 mg + glimepiride treatment group, 17.5% in the placebo + glimepiride treatment group, and 6.9% in the rosiglitazone + glimepiride treatment group.

Table 7. Results of a 26-week Trial of VICTOZA as add-on to Sulfonylurea in Adult Patients with Type 2 Diabetes Mellitusa

 | VICTOZA; 1.8 mg +; Glimepiride | VICTOZA; 1.2 mg +; Glimepiride | Placebo + Glimepiride | Rosiglitazone 4 mg† + Glimepiride
Intent-to-Treat Population (N) | 234 | 228 | 114 | 231
HbA1c (%) (Mean)
Baseline | 8.5 | 8.5 | 8.4 | 8.4
Change from baseline (adjusted mean) b | -1.1 | -1.1 | +0.2 | -0.4
Difference from placebo + glimepiride arm (adjusted mean)b | -1.4** | -1.3**
95% Confidence Interval | (-1.6, -1.1) | (-1.5, -1.1)
Percentage of patients achieving HbA1c <7% | 42 | 35 | 7 | 22
Fasting Plasma Glucose (mg/dL) (Mean)
Baseline | 174 | 177 | 171 | 179
Change from baseline (adjusted mean) b | -29 | -28 | +18 | -16
Difference from placebo + glimepiride arm (adjusted mean)b | -47** | -46**
95% Confidence Interval | (-58, -35) | (-58, -35)
Body Weight (kg) (Mean)
Baseline | 83 | 80 | 81.9 | 80.6
Change from baseline (adjusted mean) b | -0.2 | +0.3 | -0.1 | +2.1
Difference from placebo + glimepiride arm (adjusted mean)b | -0.1 | 0.4
95% Confidence Interval | (-0.9, 0.6) | (-0.4, 1.2)

a Intent-to-treat population using last observation on study

b Least squares mean adjusted for baseline value

† For rosiglitazone, one-half of the maximal approved United States dose.

** p-value <0.0001

Add-on to Metformin and Sulfonylurea

In this 26-week trial, 581 adult patients with type 2 diabetes mellitus were randomized to VICTOZA 1.8 mg, placebo, or insulin glargine, all as add-on to metformin and glimepiride. Randomization took place after a 6-week run-in period consisting of a 3-week forced metformin and glimepiride titration period followed by a maintenance period of another 3 weeks. During the titration period, doses of metformin and glimepiride were to be increased up to 2,000 mg/day and 4 mg/day, respectively. After randomization, patients randomized to VICTOZA 1.8 mg underwent a 2 week period of titration with VICTOZA. During the trial, the VICTOZA and metformin doses were fixed, although glimepiride and insulin glargine doses could be adjusted. Patients titrated glargine twice-weekly during the first 8 weeks of treatment based on self-measured fasting plasma glucose on the day of titration. After Week 8, the frequency of insulin glargine titration was left to the discretion of the investigator, but, at a minimum, the glargine dose was to be revised, if necessary, at Weeks 12 and 18. Only 20% of glargine-treated patients achieved the pre-specified target fasting plasma glucose of ≤100 mg/dL. Therefore, optimal titration of the insulin glargine dose was not achieved in most patients.

The mean age of participants was 58 years, and the mean duration of diabetes was 9 years. Participants were 56.5% male, 75.0% White and 3.6% Black or African American. The mean BMI was 30.5 kg/m^2.

Treatment with VICTOZA as add-on to glimepiride and metformin resulted in a statistically significant mean reduction in HbA1c compared to placebo add-on to glimepiride and metformin (Table 8). The percentage of patients who discontinued due to ineffective therapy was 0.9% in the VICTOZA 1.8 mg + metformin + glimepiride treatment group, 0.4% in the insulin glargine + metformin + glimepiride treatment group, and 11.3% in the placebo + metformin + glimepiride treatment group.

Table 8. Results of a 26-week Trial of VICTOZA as Add-on to Metformin and Sulfonylurea in Adult Patients with Type 2 Diabetes Mellitusa

 | VICTOZA; 1.8 mg +; Metformin +; Glimepiride | Placebo +; Metformin +; Glimepiride | Insulin glargine† +; Metformin +; Glimepiride
Intent-to-Treat Population (N) | 230 | 114 | 232
HbA1c (%) (Mean)
Baseline | 8.3 | 8.3 | 8.1
Change from baseline (adjusted mean)b | -1.3 | -0.2 | -1.1
Difference from placebo + metformin + glimepiride arm (adjusted mean)b | -1.1**
95% Confidence Interval | (-1.3, -0.9)
Percentage of patients achieving HbA1c <7% | 53 | 15 | 46
Fasting Plasma Glucose (mg/dL) (Mean)
Baseline | 165 | 170 | 164
Change from baseline (adjusted mean)b | -28 | +10 | -32
Difference from placebo + metformin + glimepiride arm (adjusted mean)b | -38**
95% Confidence Interval | (-46, -30)
Body Weight (kg) (Mean)
Baseline | 85.8 | 85.4 | 85.2
Change from baseline (adjusted mean)b | -1.8 | -0.4 | 1.6
Difference from placebo + metformin + glimepiride arm (adjusted mean)b | -1.4*
95% Confidence Interval | (-2.1, -0.7)

a Intent-to-treat population using last observation on study

b Least squares mean adjusted for baseline value

† For insulin glargine, optimal titration regimen was not achieved for 80% of patients.

* p-value <0.05

** p-value <0.0001

VICTOZA Compared to Exenatide, Both as Add-on to Metformin and/or Sulfonylurea Therapy

In this 26-week, open-label trial, 464 adult patients with type 2 diabetes mellitus on a background of metformin monotherapy, sulfonylurea monotherapy or a combination of metformin and sulfonylurea were randomized to once daily VICTOZA 1.8 mg or exenatide 10 mcg twice daily. Maximally tolerated doses of background therapy were to remain unchanged for the duration of the trial. Patients randomized to exenatide started on a dose of 5 mcg twice-daily for 4 weeks and then were escalated to 10 mcg twice-daily.

The mean age of participants was 57 years, and the mean duration of diabetes was 8 years. Participants were 51.9% male, 91.8% White, 5.4% Black or African American and 12.3% of Hispanic or Latino ethnicity. The mean BMI was 32.9 kg/m^2.

Treatment with VICTOZA 1.8 mg resulted in statistically significant reductions in HbA1c and FPG relative to exenatide (Table 9). The percentage of patients who discontinued for ineffective therapy was 0.4% in the VICTOZA treatment group and 0% in the exenatide treatment group. Both treatment groups had a mean decrease from baseline in body weight of approximately 3 kg.

Table 9. Results of a 26-week Open-label trial of VICTOZA versus Exenatide (both in combination with metformin and/or sulfonylurea) in Adult Patients with Type 2 Diabetes Mellitusa

 | VICTOZA; 1.8 mg once daily; + metformin and/or sulfonylurea | Exenatide; 10 mcg twice daily; + metformin and/or sulfonylurea
Intent-to-Treat Population (N) | 233 | 231
HbA1c (%) (Mean)
Baseline | 8.2 | 8.1
Change from baseline (adjusted mean)b | -1.1 | -0.8
Difference from exenatide arm (adjusted mean)b; 95% Confidence Interval | -0.3**; (-0.5, -0.2)
Percentage of patients achieving HbA1c <7% | 54 | 43
Fasting Plasma Glucose (mg/dL) (Mean)
Baseline | 176 | 171
Change from baseline (adjusted mean)b | -29 | -11
Difference from exenatide arm (adjusted mean)b; 95% Confidence Interval | -18**; (-25, -12)

a Intent-to-treat population using last observation carried forward

b Least squares mean adjusted for baseline value

** p-value <0.0001

Add-on to Metformin and Thiazolidinedione

In this 26-week trial, 533 adult patients with type 2 diabetes mellitus were randomized to VICTOZA 1.2 mg, VICTOZA 1.8 mg or placebo, all as add-on to rosiglitazone (8 mg) plus metformin (2,000 mg). Patients underwent a 9 week run-in period (3-week forced dose escalation followed by a 6-week dose maintenance phase) with rosiglitazone (starting at 4 mg and increasing to 8 mg/day within 2 weeks) and metformin (starting at 500 mg with increasing weekly increments of 500 mg to a final dose of 2,000 mg/day). Only patients who tolerated the final dose of rosiglitazone (8 mg/day) and metformin (2000 mg/day) and completed the 6-week dose maintenance phase were eligible for randomization into the trial.

The mean age of participants was 55 years, and the mean duration of diabetes was 9 years. Participants were 61.6% male, 84.2% White, 10.2% Black or African American and 16.4% of Hispanic or Latino ethnicity. The mean BMI was 33.9 kg/m^2.

Treatment with VICTOZA as add-on to metformin and rosiglitazone produced a statistically significant reduction in mean HbA1c compared to placebo add-on to metformin and rosiglitazone (Table 10). The percentage of patients who discontinued due to ineffective therapy was 1.7% in the VICTOZA 1.8 mg + metformin + rosiglitazone treatment group, 1.7% in the VICTOZA 1.2 mg + metformin + rosiglitazone treatment group, and 16.4% in the placebo + metformin + rosiglitazone treatment group.

Table 10. Results of a 26-week Trial of VICTOZA as Add-on to Metformin and Thiazolidinedione in Adult Patients with Type 2 Diabetes Mellitusa

 | VICTOZA; 1.8 mg +; Metformin +; Rosiglitazone | VICTOZA; 1.2 mg +; Metformin +; Rosiglitazone | Placebo + Metformin +; Rosiglitazone
Intent-to-Treat Population (N) | 178 | 177 | 175
HbA1c (%) (Mean)
Baseline | 8.6 | 8.5 | 8.4
Change from baseline (adjusted mean)b | -1.5 | -1.5 | -0.5
Difference from placebo + metformin + rosiglitazone arm (adjusted mean)b | -0.9** | -0.9**
95% Confidence Interval | (-1.1, -0.8) | (-1.1, -0.8)
Percentage of patients achieving HbA1c <7% | 54 | 57 | 28
Fasting Plasma Glucose (mg/dL) (Mean)
Baseline | 185 | 181 | 179
Change from baseline (adjusted mean)b | -44 | -40 | -8
Difference from placebo + metformin + rosiglitazone arm (adjusted mean)b | -36** | -32**
95% Confidence Interval | (-44, -27) | (-41, -23)
Body Weight (kg) (Mean)
Baseline | 94.9 | 95.3 | 98.5
Change from baseline (adjusted mean)b | -2 | -1 | +0.6
Difference from placebo + metformin + rosiglitazone arm (adjusted mean)b | -2.6** | -1.6**
95% Confidence Interval | (-3.4, -1.8) | (-2.4, -1.0)

a Intent-to-treat population using last observation on study

b Least squares mean adjusted for baseline value

** p-value <0.0001

VICTOZA Compared to Placebo Both With or Without metformin and/or Sulfonylurea and/or Pioglitazone and/or Basal or Premix insulin in Patients with Type 2 Diabetes Mellitus and Moderate Renal Impairment

In this 26-week, double-blind, randomized, placebo-controlled, parallel-group trial in adult patients with type 2 diabetes mellitus, 279 patients with moderate renal impairment, as per MDRD formula (eGFR 30-59 mL/min/1.73 m^2), were randomized to VICTOZA or placebo once daily. VICTOZA was added to the patient’s stable pre-trial antidiabetic regimen (insulin therapy and/or metformin, pioglitazone, or sulfonylurea). The dose of VICTOZA was escalated according to approved labeling to achieve a dose of 1.8 mg per day. The insulin dose was reduced by 20% at randomization for patients with baseline HbA1c ≤8% and fixed until liraglutide dose escalation was complete. Dose reduction of insulin and SU was allowed in case of hypoglycemia; up titration of insulin was allowed but not beyond the pre-trial dose.

The mean age of participants was 67 years, and the mean duration of diabetes was 15 years. Participants were 50.5% male, 92.3% White, 6.6% Black or African American, and 7.2% of Hispanic or Latino ethnicity. The mean BMI was 33.9 kg/m^2. Approximately half of patients had an eGFR between 30 and <45 mL/min/1.73 m^2.

Treatment with VICTOZA resulted in a statistically significant reduction in HbA1c from baseline at Week 26 compared to placebo (see Table 11). 123 patients reached the 1.8 mg dose of VICTOZA.

Table 11. Results of a 26-week Trial of VICTOZA Compared to Placebo in Adult Patients with Type 2 Diabetes Mellitus and Moderate Renal Impairmenta

 | VICTOZA 1.8 mg + insulin and/or OAD | Placebo + insulin and/or OAD
Intent to Treat Population (N) | 140 | 137
HbA1c (%)
Baseline (mean) | 8.1 | 8.0
Change from baseline (estimated mean)b, c | -0.9 | -0.4
Difference from placebob, c; 95% Confidence Interval | -0.6*; (-0.8, -0.3)
Proportion achieving HbA1c < 7%d | 39.3 | 19.7
FPG (mg/dL)
Baseline (mean) | 171 | 167
Change from baseline (estimated mean)e | -22 | -10
Difference from placeboe; 95% Confidence Interval | -12**; (-23, -0.8)

a Intent-to-treat population

b Estimated using a mixed model for repeated measurement with treatment, country, stratification groups as factors and baseline as a covariate, all nested within visit. Multiple imputation method modeled “wash out” of the treatment effect for patients having missing data who discontinued treatment.

c Early treatment discontinuation, before week 26, occurred in 25% and 22% of VICTOZA and placebo patients, respectively.

d Based on the known number of subjects achieving HbA1c < 7%. When applying the multiple imputation method described in b) above, the estimated percents achieving HbA1c < 7% are 47.6% and 24.9% for VICTOZA and placebo, respectively.

e Estimated using a mixed model for repeated measurement with treatment, country, stratification groups as factors and baseline as a covariate, all nested within visit.

* p-value <0.0001

** p-value <0.05

14.2 Glycemic Control Trial in Pediatric Patients Aged 10 Years and Older with Type 2 Diabetes Mellitus

VICTOZA was evaluated in a 26-week, double-blind, randomized, parallel group, placebo controlled multi-center trial (NCT01541215), in 134 pediatric patients with type 2 diabetes mellitus aged 10 years and older. Patients were randomized to VICTOZA once-daily or placebo once-daily in combination with metformin with or without basal insulin treatment. All patients were on a metformin dose of 1000 to 2000 mg prior to randomization. The basal insulin dose was decreased by 20% at randomization and VICTOZA was titrated weekly by 0.6 mg for 2 to 3 weeks based on tolerability and an average fasting plasma glucose goal of ≤110 mg/dL.

The mean age was 14.6 years: 29.9% were ages 10-14 years, and 70.1% were greater than 14 years of age. 38.1% were male, 64.9% were White, 13.4% were Asian, 11.9% were Black or African American; 29.1% were of Hispanic or Latino ethnicity. The mean BMI was 33.9 kg/m^2 and the mean BMI SDS was 2.9. 18.7% of patients were using basal insulin at baseline. The mean duration of diabetes was 1.9 years and the mean HbA1c was 7.8%.

At week 26, treatment with VICTOZA was superior in reducing HbA1c from baseline versus placebo. The estimated treatment difference in HbA1c reduction from baseline between VICTOZA and placebo was
-1.06% with a 95% confidence interval of [-1.65%; -0.46%] (see Table 12).

Table 12. Results at week 26 in a trial comparing VICTOZA in combination with metformin with or without basal insulin versus Placebo in combination with metformin with or without basal insulin in Pediatric Patients Aged 10 Years and Older with Type 2 Diabetes Mellitus

 | VICTOZA+metformin±basal insulin | Placebo+metformin±basal insulin
N | 66 | 68
HbA1c (%)
Baseline | 7.9 | 7.7
End of 26 weeks | 7.1 | 8.2
Adjusted mean change from baseline after 26 weeksa | -0.64 | 0.42
Treatment difference [95% CI]; VICTOZA vs Placebo | -1.06 [-1.65; -0.46]*
Percentage of patients achieving HbA1c <7%b | 63.7 | 36.5
FPG (mg/dL)
Baseline | 157 | 147
End of 26 weeks | 132 | 166
Adjusted mean change from baseline after 26 weeksa | -19.4 | 14.4
Treatment difference [95% CI]; VICTOZA vs Placebo | -33.83 [-55.74; -11.92]

a The change from baseline to end of treatment visit in HbA1c and FPG was analyzed using a pattern mixture model with multiple imputation. Missing observations (10.6% in the VICTOZA, 14.5% in the placebo) were imputed from the placebo arm based on multiple (x10,000) imputations. The data for week 26 was then analyzed with an ANCOVA model containing treatment, sex and age group as fixed effects and baseline value as covariate.

b Categories are derived from continuous measurements of HbA1c using a pattern mixture model with multiple imputation for missing observations.

* p-value <0.001

14.3 Cardiovascular Outcomes Trial in Adult Patients with Type 2 Diabetes Mellitus and Atherosclerotic Cardiovascular Disease

The LEADER trial (NCT01179048) was a multi-national, multi-center, placebo-controlled, double-blind trial. In this study, 9,340 adult patients with inadequately controlled type 2 diabetes mellitus and atherosclerotic cardiovascular disease (CVD) were randomized to VICTOZA 1.8 mg or placebo for a median duration of 3.5 years. The study compared the risk of major adverse cardiovascular events between VICTOZA and placebo when these were added to, and used concomitantly with, background standard of care treatments for type 2 diabetes mellitus. The primary endpoint, major adverse cardiac events (MACE), was the time to first occurrence of a three part composite outcome which included; cardiovascular death, non-fatal myocardial infarction and non-fatal stroke.

Patients eligible to enter the trial were; 50 years of age or older and had established, stable, cardiovascular, cerebrovascular, peripheral artery disease, chronic kidney disease or New York Heart Association (NYHA) class II and III heart failure (80% of the enrolled population) or were 60 years of age or older and had other specified risk factors for cardiovascular disease (20% of the enrolled population).

At baseline, demographic and disease characteristics were balanced. The mean age was 64 years and the population was 64.3% male, 77.5% White, 10.0% Asian, and 8.3% Black or African American. In the study, 12.1% of the population identified as Hispanic or Latino ethnicity. The mean duration of type 2 diabetes mellitus was 12.8 years, the mean HbA1c was 8.7% and the mean BMI was 32.5 kg/m^2. A history of previous myocardial infarction was reported in 31% of randomized individuals, a prior revascularization procedure in 39%, a prior ischemic stroke in 11%, documented symptomatic coronary disease in 9%, documented asymptomatic cardiac ischemia in 26%, and a diagnosis of NYHA class II to III heart failure in 14%. The mean eGFR at baseline was 79 mL/min/1.73 m^2 and 41.8% of patients had mild renal impairment (eGFR 60 to 90 mL/min/1.73m^2), 20.7% had moderate renal impairment (eGFR 30 to 60 mL/min/1.73 m^2) and 2.4% of patients had severe renal impairment (eGFR <30 mL/min/1.73 m^2).

At baseline, patients treated their diabetes with; diet and exercise only (3.9%), oral antidiabetic drugs only (51.5%), oral antidiabetic drugs and insulin (36.7%) or insulin only (7.9%). The most common background antidiabetic drugs used at baseline and in the trial were metformin, sulfonylurea and insulin. Use of DPP-4 inhibitors and other GLP-1 receptor agonists was excluded by protocol and sodium-glucose cotransporter-2 (SGLT-2) inhibitors were either not approved or not widely available. At baseline, cardiovascular disease and risk factors were managed with; non-diuretic antihypertensives (92.4%), diuretics (41.8%), statin therapy (72.1%) and platelet aggregation inhibitors (66.8%). During the trial, investigators could modify anti-diabetic and cardiovascular medications to achieve local standard of care treatment targets with respect to blood glucose, lipid, and blood pressure, and manage patients recovering from an acute coronary syndrome or stroke event per local treatment guidelines.

For the primary analysis, a Cox proportional hazards model was used to test for non-inferiority against the pre-specified risk margin of 1.3 for the hazard ratio of MACE and to test for superiority on MACE if non-inferiority was demonstrated. Type 1 error was controlled across multiple tests.

VICTOZA significantly reduced the occurrence of MACE. The estimated hazard ratio (95% CI) for time to first MACE was 0.87 (0.78, 0.97). Refer to Figure 5 and Table 13.

Vital status was available for 99.7% of subjects in the trial. A total of 828 deaths were recorded during the LEADER trial. A majority of the deaths in the trial were categorized as cardiovascular deaths and non-cardiovascular deaths were balanced between the treatment groups (3.5% in patients treated with VICTOZA and 3.6% in patients treated with placebo). The estimated hazard ratio of time to all-cause death for VICTOZA compared to placebo was 0.85 (0.74, 0.97).

Figure 5. Kaplan-Meier: Time to First Occurrence of a MACE in the LEADER Trial (Patients with Type 2 Diabetes Mellitus and Atherosclerotic CVD)

Table 13. Treatment Effect for the Primary Composite Endpoint, MACE, and its Components in the LEADER Trial (Patients with Type 2 Diabetes Mellitus and Atherosclerotic CVD)a

 | VICTOZA; N=4668 | Placebo; N=4672 | Hazard Ratio; (95% CI)b
Composite of cardiovascular death, non-fatal myocardial infarction, non-fatal stroke (MACE); (time to first occurrence)c | 608 (13.0%) | 694 (14.9%) | 0.87 (0.78; 0.97)
Non-fatal myocardial infarctiond | 281 (6.0%) | 317 (6.8%) | 0.88 (0.75;1.03)
Non-fatal stroked | 159 (3.4%) | 177 (3.8%) | 0.89 (0.72;1.11)
Cardiovascular deathd | 219 (4.7%) | 278 (6%) | 0.78 (0.66;0.93)

a Full analysis set (all randomized patients)

b Cox-proportional hazards model with treatment as a factor

c p-value for superiority (2-sided) 0.011

d Number and percentage of first events

16 HOW SUPPLIED/STORAGE AND HANDLING

How Supplied

VICTOZA Injection: 18 mg/3 mL (6 mg/mL) clear, colorless solution in a prefilled, single-patient-use pen that delivers doses of 0.6 mg, 1.2 mg, or 1.8 mg is available in the following package sizes:

2 x VICTOZA pen NDC 0169-4060-12

3 x VICTOZA pen NDC 0169-4060-13

Recommended Storage

Prior to first use, VICTOZA should be stored in a refrigerator between 36ºF to 46ºF (2ºC to 8ºC). Do not store in the freezer or directly adjacent to the refrigerator cooling element. Do not freeze VICTOZA and do not use VICTOZA if it has been frozen.

After first use of the VICTOZA pen, the pen can be stored for 30 days at controlled room temperature 59°F to 86°F (15°C to 30°C) or in a refrigerator 36°F to 46°F (2°C to 8°C). Keep the pen cap on when not in use. Protect VICTOZA from excessive heat and sunlight. Always remove and safely discard the needle after each injection and store the VICTOZA pen without an injection needle attached. This will reduce the potential for contamination, infection, and leakage while also ensuring dosing accuracy. Always use a new needle for each injection to prevent contamination.

17 PATIENT COUNSELING INFORMATION

Advise the patient to read the FDA-approved patient labeling (Medication Guide).

Risk of Thyroid C-cell Tumors

Inform patients that liraglutide causes benign and malignant thyroid C-cell tumors in mice and rats and that the human relevance of this finding is unknown. Counsel patients to report symptoms of thyroid tumors (e.g., a lump in the neck, hoarseness, dysphagia, or dyspnea) to their physician [see Boxed Warning, Warnings and Precautions (5.1)].

Acute Pancreatitis

Inform patients of the potential risk for acute pancreatitis and its symptoms: severe abdominal pain that may radiate to the back, and which may or may not be accompanied by nausea or vomiting. Instruct patients to discontinue VICTOZA promptly and contact their physician if pancreatitis is suspected [see Warnings and Precautions (5.2)].

Never Share a VICTOZA Pen Between Patients

Advise patients that they must never share a VICTOZA pen with another person, even if the needle is changed, because doing so carries a risk for transmission of blood-borne pathogens [see Warnings and Precautions (5.3)].

Hypoglycemia

Inform patients that hypoglycemia has been reported when VICTOZA is used with insulin secretagogues or insulin and may occur in pediatric patients regardless of concomitant antidiabetic treatment. Educate patients or caregivers on the signs and symptoms of hypoglycemia [see Warnings and Precautions (5.4)].

Acute Kidney Injury Due to Volume Depletion

Inform patients of the potential risk of acute kidney injury due to dehydration associated with gastrointestinal adverse reactions. Advise patients to take precautions to avoid fluid depletion. Inform patients of the signs and symptoms of acute kidney injury and instruct them to promptly report any of these signs or symptoms or persistent (or extended) nausea, vomiting, and diarrhea to their healthcare provider [see Warnings and Precautions (5.5)].

Severe Gastrointestinal Adverse Reactions

Inform patients of the potential risk of severe gastrointestinal adverse reactions. Instruct patients to contact their healthcare provider if they have severe or persistent gastrointestinal symptoms [see Warnings and Precautions (5.6)].

Hypersensitivity Reactions

Inform patients that serious hypersensitivity reactions have been reported during postmarketing use of VICTOZA. Advise patients on the symptoms of hypersensitivity reactions and instruct them to stop taking VICTOZA and seek medical advice promptly if such symptoms occur [see Warnings and Precautions (5.7)].

Acute Gallbladder Disease

Inform patients of the potential risk for cholelithiasis or cholecystitis. Instruct patients to contact their physician if cholelithiasis or cholecystitis is suspected for appropriate clinical follow-up [see Warnings and Precautions (5.8)].

Pulmonary Aspiration During General Anesthesia or Deep Sedation

Inform patients that VICTOZA may cause their stomach to empty more slowly which may lead to complications with anesthesia or deep sedation during planned surgeries or procedures. Instruct patients to inform healthcare providers prior to any planned surgeries or procedures if they are taking VICTOZA [see Warnings and Precautions (5.9)].

Missed Dose

Inform patients not to take an extra dose of VICTOZA to make up for a missed dose. If a dose is missed, the once-daily regimen should be resumed as prescribed with the next scheduled dose. If more than 3 days have elapsed since the last dose, advise the patient to reinitiate VICTOZA at 0.6 mg to mitigate any gastrointestinal symptoms associated with reinitiation of treatment. VICTOZA should be titrated at the discretion of the healthcare provider [see Dosage and Administration (2.2)].

Marketed by:

Novo Nordisk Inc.

Plainsboro, NJ 08536

VICTOZA® is a registered trademark of Novo Nordisk A/S.

PATENT Information: http://novonordisk-us.com/products/product-patents.html

© 2025 Novo Nordisk

For information about VICTOZA contact:

Novo Nordisk Inc.

800 Scudders Mill Road

Plainsboro, NJ 08536

1-877-484-2869

Medication Guide

VICTOZA® (VIC-tow-za)
(liraglutide) injection, for subcutaneous use

Read this Medication Guide before you start using VICTOZA and each time you get a refill. There may be new information. This information does not take the place of talking to your healthcare provider about your medical condition or your treatment.

What is the most important information I should know about VICTOZA?

VICTOZA may cause serious side effects, including:

- Possible thyroid tumors, including cancer. Tell your healthcare provider if you get a lump or swelling in your neck, hoarseness, trouble swallowing, or shortness of breath. These may be symptoms of thyroid cancer. In studies with rats and mice, VICTOZA and medicines that work like VICTOZA caused thyroid tumors, including thyroid cancer. It is not known if VICTOZA will cause thyroid tumors or a type of thyroid cancer called medullary thyroid carcinoma (MTC) in people.
- Do not use VICTOZA if you or any of your family have ever had a type of thyroid cancer called medullary thyroid carcinoma (MTC), or if you have an endocrine system condition called Multiple Endocrine Neoplasia syndrome type 2 (MEN 2).

What is VICTOZA?

VICTOZA is an injectable prescription medicine used:

- along with diet and exercise to improve blood sugar (glucose) in adults and children who are 10 years of age and older with type 2 diabetes mellitus.
- to reduce the risk of major cardiovascular events such as heart attack, stroke or death in adults with type 2 diabetes mellitus with known heart disease.
- VICTOZA is not recommended for people who take liraglutide or other medicines called glucagon-like peptide-1 (GLP-1) receptor agonists.
- It is not known if VICTOZA is safe and effective to lower blood sugar (glucose) in children under 10 years of age.

Who should not use VICTOZA?

Do not use VICTOZA if:

- you or any of your family have ever had a type of thyroid cancer called medullary thyroid carcinoma (MTC) or if you have an endocrine system condition called Multiple Endocrine Neoplasia syndrome type 2 (MEN 2).
- you have had a serious allergic reaction to liraglutide or any of the ingredients in VICTOZA. See the end of this Medication Guide for a complete list of ingredients in VICTOZA. See “What are the possible side effects of VICTOZA?” for symptoms of a serious allergic reaction.

What should I tell my healthcare provider before using VICTOZA?

Before using VICTOZA, tell your healthcare provider if you have any other medical conditions, including if you:

- have or have had problems with your pancreas.
- have severe problems with your stomach, such as slowed emptying of your stomach (gastroparesis) or problems with digesting food.
- are scheduled to have surgery or other procedures that use anesthesia or deep sleepiness (deep sedation).
- are pregnant or plan to become pregnant. It is not known if VICTOZA will harm your unborn baby. Tell your healthcare provider if you become pregnant while using VICTOZA.
- are breastfeeding or plan to breastfeed. It is not known if VICTOZA passes into your breast milk. You should talk with your healthcare provider about the best way to feed your baby while using VICTOZA.

Tell your healthcare provider about all the medicines you take, including prescription and over-the-counter medicines, vitamins, and herbal supplements. VICTOZA may affect the way some medicines work and some medicines may affect the way VICTOZA works.

Before using VICTOZA, talk to your healthcare provider about low blood sugar and how to manage it. Tell your healthcare provider if you are taking other medicines to treat diabetes, including insulin or sulfonylureas.

Know the medicines you take. Keep a list of them to show your healthcare provider and pharmacist when you get a new medicine.

How should I use VICTOZA?

- Read the Instructions for Use that comes with VICTOZA.
- Use VICTOZA exactly as your healthcare provider tells you to.
- Your healthcare provider should show you how to use VICTOZA before you use it for the first time.
- Inject your dose of VICTOZA under the skin (subcutaneously) of your stomach (abdomen), thigh, or upper arm. Do not inject VICTOZA into a muscle (intramuscularly) or vein (intravenously).
- Use VICTOZA 1 time each day, at any time of the day.
- If you miss a dose of VICTOZA, take the missed dose at the next scheduled dose. Do not take 2 doses of VICTOZA at the same time.
- VICTOZA may be taken with or without food.
- Donot mix insulin and VICTOZA together in the same injection.
- You may give an injection of VICTOZA and insulin in the same body area (such as your stomach area), but not right next to each other.
- Change (rotate) your injection site with each injection. Do not use the same site for each injection.
- Do not share your VICTOZA pen with other people, even if the needle has been changed. You may give other people a serious infection or get a serious infection from them.
- If you take too much VICTOZA, call your healthcare provider or the Poison Help line at 1-800-222-1222 or go to the nearest hospital emergency room right away.
- The VICTOZA pen you are using should be thrown away 30 days after you start using it.

What are the possible side effects of VICTOZA?

VICTOZA may cause serious side effects, including:

- See “What is the most important information I should know about VICTOZA?”
- inflammation of your pancreas (pancreatitis). Stop using VICTOZA and call your healthcare provider right away if you have severe pain in your stomach area (abdomen) that will not go away, with or without vomiting. You may feel the pain from your abdomen to your back.
- low blood sugar (hypoglycemia). Your risk for getting low blood sugar may be higher if you use VICTOZA with another medicine that can cause low blood sugar, such as a sulfonylurea or insulin. In children who are 10 years of age and older, the risk for low blood sugar may be higher with VICTOZA regardless of use with another medicine that can also lower blood sugar.

Signs and symptoms of low blood sugar may include:

- dizziness or light-headedness
- sweating
- confusion or drowsiness
- headache

- blurred vision
- slurred speech
- shakiness
- fast heartbeat

- anxiety, irritability, or mood changes
- hunger
- weakness
- feeling jittery

- dehydration leading to kidney problems. Diarrhea, nausea, and vomiting may cause a loss of fluids (dehydration) which may cause kidney problems. It is important for you to drink fluids to help reduce your chance of dehydration. Tell your healthcare provider right away if you have nausea, vomiting, or diarrhea that does not go away.
- severe stomach problems. Stomach problems, sometimes severe, have been reported in people who use VICTOZA. Tell your healthcare provider if you have stomach problems that are severe or will not go away.
- serious allergic reactions. Stop using VICTOZA and get medical help right away if you have any symptoms of a serious allergic reaction including:

- swelling of your face, lips, tongue or throat
- problems breathing or swallowing
- severe rash or itching

- fainting or feeling dizzy
- very rapid heartbeat

- gallbladder problems. Gallbladder problems have happened in some people who take VICTOZA. Tell your healthcare provider right away if you get symptoms of gallbladder problems which may include:

- pain in your upper stomach (abdomen)
- fever

- yellowing of skin or eyes (jaundice)
- clay-colored stools

- food or liquid getting into the lungs during surgery or other procedures that use anesthesia or deep sleepiness (deep sedation). VICTOZA may increase the chance of food getting into your lungs during surgery or other procedures. Tell all your healthcare providers that you are taking VICTOZA before you are scheduled to have surgery or other procedures.

The most common side effects of VICTOZA may include nausea, diarrhea, vomiting, decreased appetite, indigestion and constipation.

Talk to your healthcare provider about any side effect that bothers you or does not go away. These are not all the possible side effects of VICTOZA.

Call your doctor for medical advice about side effects. You may report side effects to FDA at 1-800-FDA-1088.

General information about the safe and effective use of VICTOZA.

Medicines are sometimes prescribed for purposes other than those listed in a Medication Guide. Do not use VICTOZA for a condition for which it was not prescribed. Do not give VICTOZA to other people, even if they have the same symptoms that you have. It may harm them. If you would like more information, talk with your healthcare provider. You can ask your pharmacist or healthcare provider for information about VICTOZA that is written for health professionals.

What are the ingredients in VICTOZA?

Active ingredient: liraglutide

Inactive ingredients: disodium phosphate dihydrate, propylene glycol, phenol and water for injection. Hydrochloric acid or sodium hydroxide may be added to adjust pH

Manufactured by: Novo Nordisk A/S, DK-2880 Bagsvaerd, Denmark Victoza® is a registered trademark of Novo Nordisk A/S.

For more information, go to victoza.com or call 1-877-484-2869. PATENT Information: http://novonordisk-us.com/patients/products/product-patents.html

© 2025 Novo Nordisk

This Medication Guide has been approved by the U.S. Food and Drug Administration. Revised: 05//2025

Instructions for Use

Victoza (liraglutide) injection

First read the Medication Guide that comes with your Victoza single-patient use pen and then read this Instructions for Use for information about how to use your Victoza pen the right way.

These instructions do not take the place of talking with your healthcare provider about your medical condition or your treatment.

Do not share your Victoza Pen with other people, even if the needle has been changed. You may give other people a serious infection, or get a serious infection from them.

Your Victoza pen is a disposable single-patient-use prefilled pen injector that contains 3 mL of Victoza and will deliver doses of 0.6 mg, 1.2 mg or 1.8 mg. The number of doses that you can take with a Victoza pen depends on the dose of medicine that is prescribed for you. Your healthcare provider will tell you how much Victoza to take.

Talk to your healthcare provider or pharmacist for more information about needles for your Victoza pen.

Important Information

Always use a new needle for each injection to prevent contamination.

Always remove the needle after each injection, and store your pen without the needle attached. This reduces the risk of contamination, infection, leakage of liraglutide, blocked needles and inaccurate dosing.

Keep your Victoza pen and all medicines out of the reach of children.

If you drop your Victoza pen, repeat “First Time Use for Each New Pen” (steps A through D).

Be careful not to bend or damage the needle.

Do not use the cartridge scale to measure how much Victoza to inject.

Be careful when handling used needles to avoid needle stick injuries.

You can use your Victoza pen for up to 30 days after you use it the first time.

Supplies you will need to give your Victoza injection:

- Victoza pen
- a new disposable needle
- alcohol swab
- cotton ball or gauze
- sharps disposal container for throwing away used Victoza pens and needles.

See “Remove and Dispose of the Needle” at the end of these instructions.

First Time Use for Each New Pen

Step A. Check the Pen

- Take your new Victoza pen out of the refrigerator.
- Wash hands with soap and water before use.
- Check pen label before each use to make sure it is your Victoza pen.
- Pull off pen cap (See Figure A).
- Check Victoza in the cartridge. The liquid should be clear, colorless and free of particles. If not, do not use.
- Wipe the rubber stopper with an alcohol swab.

Step B. Attach the Needle

- Remove protective tab from outer needle cap.
- Push outer needle cap containing the needle straight onto the pen, then screw needle on until secure.
(See Figure B).

- Pull off outer needle cap. (See Figure C). Do not throw away

- Pull off inner needle cap and throw away. (See Figure D). A small drop of liquid may appear. This is normal.

Step C. Dial to the Flow Check Symbol

This step is done only One Time for each new pen and is Only required the first time you use a new pen.

- Turn dose selector until flow check symbol (--) lines up with pointer (See Figure E). The flow check symbol does not administer the dose as prescribed by your healthcare provider.
- To select the dose prescribed by your healthcare provider, continue to Step G under “Routine Use”.

Step D. Prepare the Pen

- Hold pen with needle pointing up.
- Tap cartridge gently with your finger a few times to bring any air bubbles to the top of the cartridge (See Figure F).

- Keep needle pointing up and press dose button until 0 mg lines up with pointer (See Figure G). Repeat steps C and D, up to 6 times, until a drop of Victoza appears at the needle tip.

If you still see no drop of Victoza, use a new pen and contact Novo Nordisk at 1-877-484-2869.

Continue to Step G under “Routine Use”

Routine Use

Step E. Check the Pen

- Take your Victoza pen from where it is stored.
- Wash hands with soap and water before use.
- Check pen label before each use to make sure it is your Victoza pen.
- Pull off pen cap (See Figure H).
- Check Victoza in the cartridge. The liquid should be clear, colorless and free of particles. If not, do not use.
- Wipe the rubber stopper with an alcohol swab.

Step F. Attach the Needle

- Remove protective tab from outer needle cap.
- Push outer needle cap containing the needle straight onto the pen, then screw needle on until secure (See Figure I).

- Pull off outer needle cap. Do not throw away (See Figure J).

- Pull off inner needle cap and throw away (See Figure K). A small drop of liquid may appear. This is normal.

Step G. Dial the Dose

- Victoza pen can give a dose of 0.6 mg (starting dose), 1.2 mg or 1.8 mg. Be sure that you know the dose of Victoza that is prescribed for you.
- Turn the dose selector until your needed dose lines up with the pointer (0.6 mg,
1.2 mg or 1.8 mg) (See Figure L).

- You will hear a “click” every time you turn the dose selector. Do not set the dose by counting the number of clicks you hear.

- If you select a wrong dose, change it by turning the dose selector backwards or forwards until the correct dose lines up with the pointer. Be careful not to press the dose button when turning the dose selector. This may cause Victoza to come out.

Step H. Injecting the Dose

- Choose your injection site in either the stomach (abdomen), thigh, or upper arm (only if caregiver administered) and wipe the skin with an alcohol swab (See Figure M). Let the injection site dry before you inject your dose.
- Insert needle into your skin using the injection technique shown to you by your healthcare provider. Do not inject Victoza into a vein or muscle.

- Press down on the center of the dose button to inject until 0 mg lines up with the pointer (See Figure N).

- Be careful not to touch the dose display with your other fingers. This may block the injection.

- Keep the dose button pressed down and make sure that you keep the needle under the skin for a full count of 6 seconds to make sure the full dose is injected. Keep your thumb on the injection button until you remove the needle from your skin (See Figure O).

- Change (rotate) your injection sites within the area you choose for each dose. Do not use the same injection site for each injection.

Step I. Withdraw Needle

- You may see a drop of Victoza at the needle tip. This is normal and it does not affect the dose you just received. If blood appears after you take the needle out of your skin, apply light pressure with a cotton ball or gauze, but do not rub the area (See Figure P).

Step J. Remove and Dispose of the Needle

- Carefully put the outer needle cap over the needle (See Figure Q). Unscrew the needle.
- Safely remove the needle from your Victoza pen after each use.

- Put your used VICTOZA pen and needles in a FDA-cleared sharps disposal container right away after use. Do not throw away (dispose of) loose needles and pens in your household trash.
- If you do not have a FDA-cleared sharps disposal container, you may use a household container that is:
- made of a heavy-duty plastic
- can be closed with a tight-fitting, puncture-resistant lid, without sharps being able to come out
- upright and stable during use
- leak-resistant
- properly labeled to warn of hazardous waste inside the container
- When your sharps disposal container is almost full, you will need to follow your community guidelines for the right way to dispose of your sharps disposal container. There may be state or local laws about how you should throw away used needles and syringes. Do not reuse or share your needles with other people. For more information about the safe sharps disposal, and for specific information about sharps disposal in the state that you live in, go to the FDA’s website at: http://www.fda.gov/safesharpsdisposal.
- Do not dispose of your used sharps disposal container in your household trash unless your community guidelines permit this. Do not recycle your used sharps disposal container.

Caring for your Victoza pen

- After removing the needle, put the pen cap on your Victoza pen and store your Victoza pen without the needle attached (See Figure R).
- Do not try to refill your Victoza pen – it is prefilled and is disposable.

- Do not try to repair your pen or pull it apart.
- Keep your Victoza pen away from dust, dirt and liquids.
- If cleaning is needed, wipe the outside of the pen with a clean, damp cloth.

How should I store Victoza?

Before use:
2. Store your new, unused Victoza pen in the refrigerator between 36ºF to 46ºF (2ºC to 8ºC).
3. If Victoza is stored outside of refrigeration (by mistake) prior to first use, it should be used or thrown away within 30 days.
4. Do not freeze Victoza or use Victoza if it has been frozen. Do not store Victoza near the refrigerator cooling element.
Pen in use:
6. Use a Victoza pen for only 30 days. Throw away a used Victoza pen 30 days after you start using it, even if some medicine is left in the pen.
7. Store your Victoza pen at room temperature between 59ºF to 86ºF (15ºC to 30ºC), or in a refrigerator between 36ºF to 46ºF (2°C to 8°C).
8. When carrying the pen away from home, store the pen at room temperature between 59ºF to 86ºF (15ºC to 30ºC).
9. If Victoza has been exposed to temperatures above 86ºF (30ºC), it should be thrown away.
10. Protect your Victoza pen from heat and sunlight.
11. Keep the pen cap on when your Victoza pen is not in use.
12. Always remove the needle after each injection and store your pen without the needle attached. This reduces the risk of contamination, infection, leakage and inaccurate dosing.

This Instructions for Use has been approved by the U.S. Food and Drug Administration. Revised: 02/2025

Principal Display Panel - 3 Victoza Pens

NDC 0169-4060-13

List 406013

VICTOZA®

(liraglutide) injection

For Single Patient Use Only

18 mg/3 mL (6 mg/mL)

Each pen delivers doses of 0.6 mg, 1.2 mg or 1.8 mg

Subcutaneous use only

Discard pen 30 days after first use

REFRIGERATE - DO NOT FREEZE

Rx Only

Contains: 3 Victoza Pens, Product Literature

Dispense the enclosed Medication Guide to each patient

Pen needles not included

3 Pens

Principal Display Panel - 2 Victoza Pens

NDC 0169-4060-12

List 406012

VICTOZA®

(liraglutide) injection

For Single Patient Use Only

18 mg/3 mL (6 mg/mL)

Each pen delivers doses of 0.6 mg, 1.2 mg or 1.8 mg

Subcutaneous use only

Discard pen 30 days after first use

REFRIGERATE - DO NOT FREEZE

Rx Only

Contains: 2 Victoza Pens, Product Literature

Dispense the enclosed Medication Guide to each patient

Pen needles not included

2 Pens